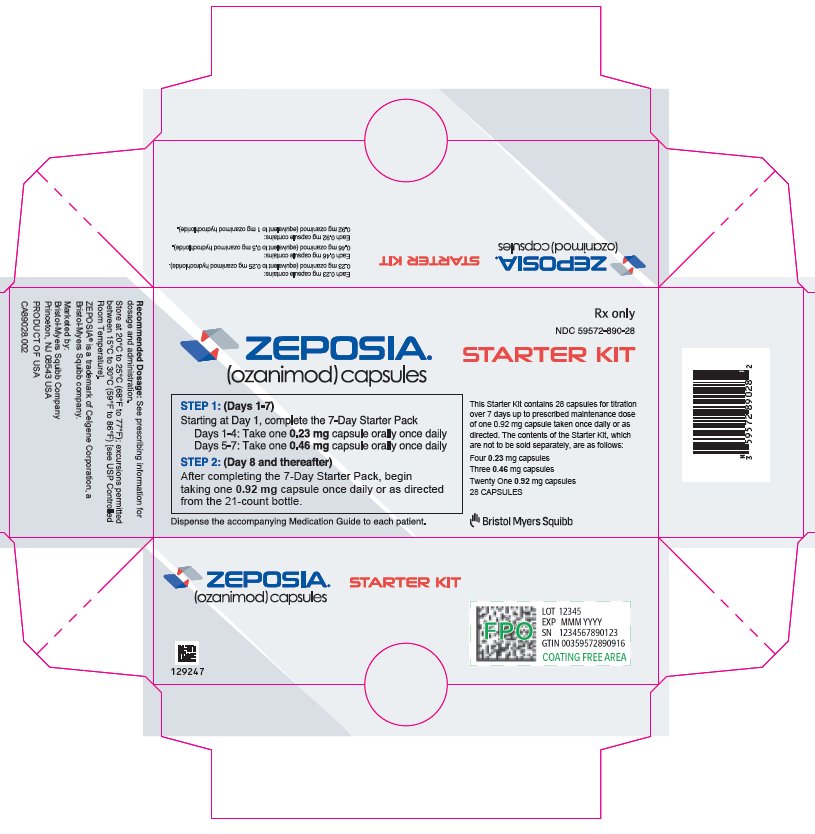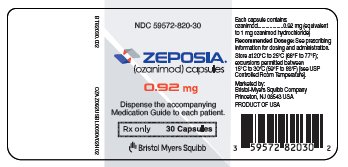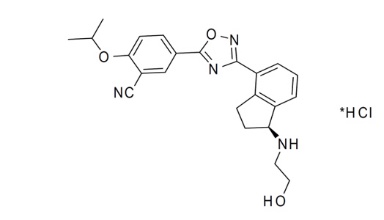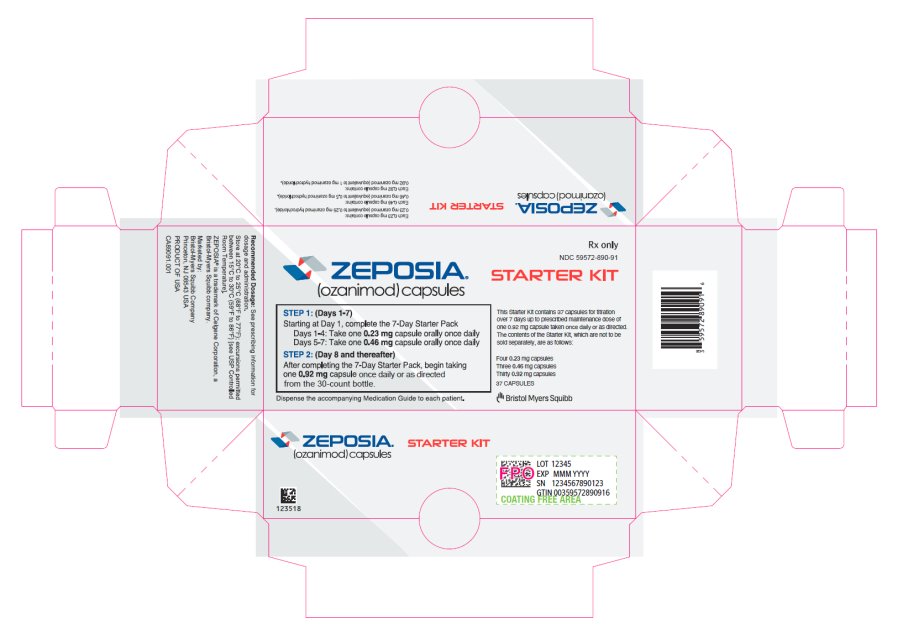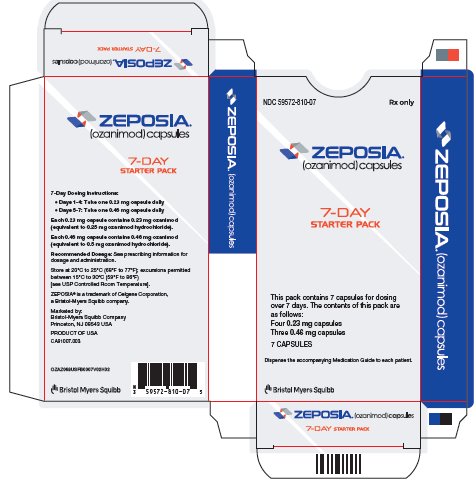 DRUG LABEL: ZEPOSIA
NDC: 59572-820 | Form: CAPSULE
Manufacturer: Celgene Corporation
Category: prescription | Type: HUMAN PRESCRIPTION DRUG LABEL
Date: 20240830

ACTIVE INGREDIENTS: OZANIMOD HYDROCHLORIDE 0.92 mg/1 1
INACTIVE INGREDIENTS: MICROCRYSTALLINE CELLULOSE; CROSCARMELLOSE SODIUM; SILICON DIOXIDE; MAGNESIUM STEARATE

HIGHLIGHTS OF PRESCRIBING INFORMATION

These highlights do not include all the information needed to use ZEPOSIA safely and effectively. See full prescribing information for ZEPOSIA.
ZEPOSIA® (ozanimod) capsules, for oral use
Initial U.S. Approval: 2020

RECENT MAJOR CHANGES

Dosage and Administration (2.1) 6/2024

Warnings and Precautions (5.2, 5.8, 5.9) 6/2024

Warnings and Precautions (5.4, 5.6) 8/2024

1 INDICATIONS AND USAGE

ZEPOSIA is a sphingosine 1-phosphate receptor modulator indicated for the treatment of:

- Relapsing forms of multiple sclerosis (MS), to include clinically isolated syndrome, relapsing-remitting disease, and active secondary progressive disease, in adults. (1)
- Moderately to severely active ulcerative colitis (UC) in adults. (1)

2 DOSAGE AND ADMINISTRATION

- Assessments are required prior to initiating ZEPOSIA. (2.1)
- Titration is required for treatment initiation. (2.2)
- The recommended maintenance dosage is 0.92 mg orally once daily. (2.2)
- The recommended maintenance dosage in patients with mild or moderate chronic hepatic impairment (Child-Pugh class A or B) is 0.92 mg once every other day. (2.3)
- If a dose is missed within the first 2 weeks of treatment, reinitiate with the titration regimen. If a dose is missed after the first 2 weeks of treatment, continue treatment as planned. (2.4)

3 DOSAGE FORMS AND STRENGTHS

Capsules: 0.23 mg, 0.46 mg, 0.92 mg ozanimod (3)

4 CONTRAINDICATIONS

- In the last 6 months, experienced myocardial infarction, unstable angina, stroke, transient ischemic attack, decompensated heart failure requiring hospitalization, or Class III or IV heart failure. (4)
- Presence of Mobitz type II second-degree or third degree atrioventricular (AV) block, sick sinus syndrome, or sino-atrial block, unless the patient has a functioning pacemaker. (4)
- Severe untreated sleep apnea. (4)
- Concomitant use of a monoamine oxidase inhibitor. (4, 7)

5 WARNINGS AND PRECAUTIONS

- Infections: ZEPOSIA may increase the risk of infections. Obtain a complete blood count (CBC) before initiation of treatment. Monitor for infection during treatment and for 3 months after discontinuation. Do not start ZEPOSIA in patients with active infections. (5.1)
- Progressive Multifocal Leukoencephalopathy (PML): Withhold ZEPOSIA at the first sign or symptom suggestive of PML. (5.2)
- Bradyarrhythmia and Atrioventricular Conduction Delays: ZEPOSIA may result in transient decrease in heart rate; titration is required for treatment initiation. Check an electrocardiogram (ECG) to assess for preexisting cardiac conduction abnormalities before starting ZEPOSIA. Consider cardiology consultation for conduction abnormalities or concomitant use with other drugs that decrease heart rate. (2.1, 2.2, 5.3, 7)
- Liver Injury: Obtain liver enzyme results before initiation and periodically during treatment. Discontinue if there is evidence of liver injury without other cause. (5.4)
- Fetal Risk: Women of childbearing potential should use effective contraception during treatment and for 3 months after stopping ZEPOSIA. (5.5, 8.3)
- Increased Blood Pressure (BP): Monitor BP during treatment. (5.6)
- Respiratory Effects: May cause a decline in pulmonary function. Assess pulmonary function (e.g., spirometry) if clinically indicated. (5.7)
- Macular Edema: Increases the risk of macular edema. Obtain a baseline evaluation of the fundus, including the macula, near the start of treatment with ZEPOSIA. Conduct an evaluation of the fundus, including the macula, periodically while on therapy and any time there is a change in vision. Consider discontinuing ZEPOSIA if macular edema develops. Diabetes mellitus and uveitis increase the risk. (5.8)
- Cutaneous Malignancies: Skin examination prior to or shortly after the start of treatment and periodically thereafter is recommended. Suspicious skin lesions should be evaluated. (5.9)

6 ADVERSE REACTIONS

Most common adverse reactions (incidence ≥4%) are:

- Multiple Sclerosis: upper respiratory infection, hepatic transaminase elevation, orthostatic hypotension, urinary tract infection, back pain, and hypertension. (6.1)
- Ulcerative Colitis: liver test increased, upper respiratory infection, and headache. (6.1)

To report SUSPECTED ADVERSE REACTIONS, contact Bristol-Myers Squibb at 1-800-721-5072 or FDA at 1-800-FDA-1088 or www.fda.gov/medwatch.

7 DRUG INTERACTIONS

- Vaccination: Avoid use of live attenuated vaccines during and for up to 3 months after treatment with ZEPOSIA. (7)
- See full prescribing information for a list of clinically important drug interactions. (7)

8 USE IN SPECIFIC POPULATIONS

Hepatic Impairment: Use in severe hepatic impairment (Child-Pugh class C) is not recommended. (2.3, 8.6)

FULL PRESCRIBING INFORMATION

1 INDICATIONS AND USAGE

ZEPOSIA is indicated for the treatment of:

- relapsing forms of multiple sclerosis (MS), to include clinically isolated syndrome, relapsing-remitting disease, and active secondary progressive disease, in adults.
- moderately to severely active ulcerative colitis (UC) in adults.

2 DOSAGE AND ADMINISTRATION

2.1 Assessments Prior to First Dose of ZEPOSIA

Before initiation of treatment with ZEPOSIA, assess the following:

Cardiac Evaluation

Obtain an electrocardiogram (ECG) to determine whether preexisting conduction abnormalities are present. In patients with certain preexisting conditions, advice from a cardiologist should be sought [see Warnings and Precautions (5.3)].

Complete Blood Count

Obtain a recent (i.e., within the last 6 months or after discontinuation of prior MS or UC therapy) complete blood count (CBC), including lymphocyte count [see Warnings and Precautions (5.1)].

Liver Function Tests

Obtain recent (i.e., within the last 6 months) transaminase and bilirubin levels [see Warnings and Precautions (5.4)].

Ophthalmic Assessment

Obtain a baseline evaluation of the fundus, including the macula, near the start of treatment with ZEPOSIA [see Warnings and Precautions (5.8)].

Skin Examination

Obtain a baseline skin examination prior to or shortly after initiation of ZEPOSIA. If a suspicious skin lesion is observed, it should be promptly evaluated [see Warnings and Precautions (5.9)].

Current or Prior Medications

- If patients are taking anti-neoplastic, non-corticosteroid immunosuppressive, or immune-modulating therapies, or if there is a history of prior use of these drugs, consider possible unintended additive immunosuppressive effects before initiating treatment with ZEPOSIA [see Warnings and Precautions (5.1) and Drug Interactions (7)].
- Determine if patients are taking drugs that could slow heart rate or atrioventricular conduction [see Warnings and Precautions (5.3) and Drug Interactions (7)].

Vaccinations

Patients without a healthcare professional-confirmed history of chickenpox or without documentation of a full course of vaccination against varicella zoster virus (VZV) should be tested for antibodies to VZV before initiating ZEPOSIA; VZV vaccination of antibody-negative patients is recommended prior to commencing treatment with ZEPOSIA [see Warnings and Precautions (5.1) and Drug Interactions (7)].

If live attenuated vaccine immunizations are required, administer at least 1 month prior to initiation of ZEPOSIA.

2.2 Recommended Dosage for Multiple Sclerosis and Ulcerative Colitis

Initiate ZEPOSIA with a 7-day titration, as shown in Table 1 [see Warnings and Precautions (5.3)]. After initial titration, the recommended dosage of ZEPOSIA is 0.92 mg taken orally once daily starting on Day 8.

Swallow ZEPOSIA capsules whole, with or without food [see Clinical Pharmacology (12.3)].

Table 1: Dose Titration Regimen
Days 1-4 | 0.23 mg once daily
Days 5-7 | 0.46 mg once daily
Day 8 and thereafter | 0.92 mg once daily*

*Patients with mild to moderate hepatic impairment (Child-Pugh class A or B) should take 0.92 mg once every other day [see Recommended Dosage in Patients with Hepatic Impairment (2.3).]

2.3 Recommended Dosage in Patients with Hepatic Impairment

In patients with mild or moderate hepatic impairment (Child-Pugh class A or B), initiate ZEPOSIA with a 7-day titration, as shown in Table 1. After initial titration, the recommended dosage of ZEPOSIA in these patients is 0.92 mg taken orally once every other day, starting on Day 8 [see Use in Specific Populations (8.6) and Clinical Pharmacology (12.3)].

2.4 Reinitiation of ZEPOSIA after Treatment Interruption

If a dose of ZEPOSIA is missed during the first 2 weeks of treatment, reinitiate treatment using the titration regimen [see Dosage and Administration (2.2)].

If a dose of ZEPOSIA is missed after the first 2 weeks of treatment, continue with the treatment as planned.

3 DOSAGE FORMS AND STRENGTHS

Capsules:

- 0.23 mg ozanimod: light grey opaque body/light grey opaque cap imprinted with black ink "OZA" on the cap and "0.23 mg" on the body
- 0.46 mg ozanimod: light grey opaque body/orange opaque cap imprinted with black ink "OZA" on the cap and "0.46 mg" on the body
- 0.92 mg ozanimod: orange opaque body/orange opaque cap imprinted with black ink "OZA" on the cap and "0.92 mg" on the body

4 CONTRAINDICATIONS

ZEPOSIA is contraindicated in patients who:

- In the last 6 months, have experienced a myocardial infarction, unstable angina, stroke, transient ischemic attack (TIA), decompensated heart failure requiring hospitalization, or Class III or IV heart failure [see Warnings and Precautions (5.3)]
- Have the presence of Mobitz type II second-degree or third degree atrioventricular (AV) block, sick sinus syndrome, or sino-atrial block, unless the patient has a functioning pacemaker [see Warnings and Precautions (5.3)]
- Have severe untreated sleep apnea [see Warnings and Precautions (5.3)]
- Are taking a monoamine oxidase (MAO) inhibitor [see Drug Interactions (7)]

5 WARNINGS AND PRECAUTIONS

5.1 Infections

Risk of Infections

ZEPOSIA causes a mean reduction in peripheral blood lymphocyte count to approximately 45% of baseline values because of reversible sequestration of lymphocytes in lymphoid tissues [see Clinical Pharmacology (12.2)]. ZEPOSIA may therefore increase the susceptibility to infections, some serious in nature. Life-threatening and rare fatal infections have occurred in patients receiving ZEPOSIA.

Obtain a recent (i.e., within 6 months or after discontinuation of prior MS or UC therapy) complete blood count (CBC) including lymphocyte count before initiation of ZEPOSIA.

Delay initiation of ZEPOSIA in patients with an active infection until the infection is resolved.

In MS Study 1 and Study 2, the overall rate of infections and rate of serious infections in patients treated with ZEPOSIA were similar to that in patients who received interferon (IFN) beta-1a (35% vs. 34% and 1% vs. 0.8%, respectively). In UC Study 1 and Study 3, the overall rate of infections and rate of serious infections in patients treated with ZEPOSIA were similar to that in patients who received placebo (9.9% vs. 10.7% and 0.8% vs. 0.4%, respectively). In UC Study 2, the overall rate of infections in patients treated with ZEPOSIA was higher than in patients treated with placebo (23% vs. 12%) and the rate of serious infections was similar (0.9% vs. 1.8%).

ZEPOSIA increased the risk of viral upper respiratory tract infections, urinary tract infections, and herpes infections [see Adverse Reactions (6.1)].

The proportion of patients treated with ZEPOSIA who experienced lymphocyte counts less than 0.2 × 10^9/L was 3.3% in MS Study 1 and Study 2. The proportion of patients treated with ZEPOSIA with lymphocyte counts less than 0.2 × 10^9/L was 2% in UC Study 1 and Study 3 and 2.3% in UC Study 2. These values generally returned to greater than 0.2 × 10^9/L while patients remained on treatment with ZEPOSIA. After discontinuing ZEPOSIA 0.92 mg, the median time for peripheral blood lymphocytes to return to the normal range was approximately 30 days, with approximately 80% to 90% of patients in the normal range within 3 months [see Clinical Pharmacology (12.2)].

Consider interruption of treatment with ZEPOSIA if a patient develops a serious infection.

Because the elimination of ZEPOSIA after discontinuation may take up to 3 months, continue monitoring for infections throughout this period.

Herpes Viral Infection

Cases of localized herpes virus infection (e.g., herpes zoster and herpes simplex) were seen in clinical trials of ZEPOSIA.

In MS Study 1 and Study 2, herpes zoster was reported as an adverse reaction in 0.6% of patients treated with ZEPOSIA 0.92 mg and in 0.2% of patients who received IFN beta-1a.

In UC Study 1 and Study 3, herpes zoster was reported in 0.4% of patients who received ZEPOSIA and none in patients who received placebo. In UC Study 2, herpes zoster was reported in 2.2% of patients who received ZEPOSIA and 0.4% of patients who received placebo. None were serious or disseminated.

Herpes simplex encephalitis and varicella zoster meningitis have been reported with sphingosine 1-phosphate (S1P) receptor modulators. Patients without a healthcare professional-confirmed history of varicella (chickenpox), or without documentation of a full course of vaccination against varicella zoster virus (VZV), should be tested for antibodies to VZV before initiating ZEPOSIA (see Vaccinations below).

Cryptococcal Infection

Cases of fatal cryptococcal meningitis (CM) and disseminated cryptococcal infections have been reported with S1P receptor modulators. Physicians should be vigilant for clinical symptoms or signs of CM. Patients with symptoms or signs consistent with a cryptococcal infection should undergo prompt diagnostic evaluation and treatment. ZEPOSIA treatment should be suspended until a cryptococcal infection has been excluded. If CM is diagnosed, appropriate treatment should be initiated.

Prior and Concomitant Treatment with Anti-Neoplastic, Non-Corticosteroid Immunosuppressive, or Immune-modulating Therapies

In the MS and UC clinical studies, patients who received ZEPOSIA were not to receive concomitant treatment with anti-neoplastic, non-corticosteroid immunosuppressive, or immune-modulating therapies used for the treatment of MS and UC. Concomitant use of ZEPOSIA with any of these therapies would be expected to increase the risk of immunosuppression. In UC studies, concomitant use of corticosteroids was allowed and did not appear to influence the safety or efficacy of ZEPOSIA [see Clinical Studies (14.2)].

Anti-neoplastic, immune-modulating, or immunosuppressive therapies (including corticosteroids) should be co-administered with caution because of the risk of additive immune system effects during such therapy. When switching to ZEPOSIA from immunosuppressive medications, consider the duration of their effects and their mode of action to avoid unintended additive immunosuppressive effects.

Vaccinations

Patients without a healthcare professional-confirmed history of chickenpox or without documentation of a full course of vaccination against VZV should be tested for antibodies to VZV before initiating ZEPOSIA. A full course of vaccination for antibody-negative patients with varicella vaccine is recommended prior to commencing treatment with ZEPOSIA, following which initiation of treatment with ZEPOSIA should be postponed for 4 weeks to allow the full effect of vaccination to occur.

No clinical data are available on the efficacy and safety of vaccinations in patients taking ZEPOSIA. Vaccinations may be less effective if administered during ZEPOSIA treatment.

If live attenuated vaccine immunizations are required, administer at least 1 month prior to initiation of ZEPOSIA. Avoid the use of live attenuated vaccines during and for 3 months after treatment with ZEPOSIA.

5.2 Progressive Multifocal Leukoencephalopathy

Progressive multifocal leukoencephalopathy (PML) is an opportunistic viral infection of the brain caused by the JC virus (JCV) that typically occurs in patients who are immunocompromised, and that usually leads to death or severe disability. Typical symptoms associated with PML are diverse, progress over days to weeks, and include progressive weakness on one side of the body or clumsiness of limbs, disturbance of vision, and changes in thinking, memory, and orientation leading to confusion and personality changes.

PML has been reported in patients treated with S1P receptor modulators, including ZEPOSIA, and other multiple sclerosis (MS) and UC therapies and has been associated with some risk factors (e.g., immunocompromised patients, polytherapy with immunosuppressants, duration of use). Based on data from patients with MS, longer treatment duration increases the risk of PML in patients treated with S1P receptor modulators, and the majority of PML cases have occurred in patients treated with S1P receptor modulators for at least 18 months. Physicians should be vigilant for clinical symptoms or MRI findings that may be suggestive of PML. MRI findings may be apparent before clinical signs or symptoms. If PML is suspected, treatment with ZEPOSIA should be suspended until PML has been excluded by an appropriate diagnostic evaluation.

If PML is confirmed, treatment with ZEPOSIA should be discontinued.

Immune reconstitution inflammatory syndrome (IRIS) has been reported in MS patients treated with S1P receptor modulators who developed PML and subsequently discontinued treatment. IRIS presents as a clinical decline in the patient’s condition that may be rapid, can lead to serious neurological complications or death, and is often associated with characteristic changes on MRI. The time to onset of IRIS in patients with PML was generally within a few months after S1P receptor modulator discontinuation. Monitoring for development of IRIS and appropriate treatment of the associated inflammation should be undertaken.

5.3 Bradyarrhythmia and Atrioventricular Conduction Delays

Since initiation of ZEPOSIA may result in a transient decrease in heart rate and atrioventricular conduction delays, an up-titration scheme should be used to reach the maintenance dosage of ZEPOSIA [see Dosage and Administration (2.2) and Clinical Pharmacology (12.2)].

ZEPOSIA was not studied in patients who had:

- A myocardial infarction, unstable angina, stroke, TIA, or decompensated heart failure requiring hospitalization within the last 6 months
- New York Heart Association Class III / IV heart failure
- Cardiac conduction or rhythm disorders, including sick sinus syndrome, significant QT prolongation (QTcF > 450 msec in males, > 470 msec in females), risk factors for QT prolongation, or other conduction abnormalities or cardiac condition that in the opinion of the treating investigator could jeopardize the patient's health
- Other pre-existing stable cardiac conditions without clearance from a cardiologist
- Severe untreated sleep apnea
- A resting heart rate less than 55 beats per minute (bpm) at baseline

Reduction in Heart Rate

Initiation of ZEPOSIA may result in a transient decrease in heart rate. After the initial dose of ZEPOSIA 0.23 mg, the greatest mean decrease from baseline in heart rate occurred at Hour 5 on Day 1 (decrease of 1.2 bpm in MS Study 1 and Study 2, and 0.7 bpm in UC Study 1 and Study 3), returning to near baseline at Hour 6. With continued up-titration, the maximal heart rate effect of ozanimod occurred on Day 8. The utility of performing first-dose cardiac monitoring when initiating ZEPOSIA in patients with characteristics similar to those studied in the clinical trials of ZEPOSIA is unclear. Heart rates below 40 bpm were not observed. Initiation of ZEPOSIA without titration may result in greater decreases in heart rate [see Dosage and Administration (2.2)].

In MS Study 1 and Study 2, bradycardia was reported on the day of treatment initiation in 0.6% of patients treated with ZEPOSIA compared to no patients who received IFN beta-1a. After Day 1, the incidence of bradycardia was 0.8% in patients treated with ZEPOSIA compared to 0.7% of patients who received IFN beta-1a. In UC Study 1 and Study 3, bradycardia was reported on the day of treatment initiation in 1 patient (0.2%) treated with ZEPOSIA compared to none in patients who received placebo. After Day 1, bradycardia was reported in 1 patient (0.2%) treated with ZEPOSIA. In UC Study 2, bradycardia was not reported.

Atrioventricular Conduction Delays

Initiation of ZEPOSIA may result in transient atrioventricular conduction delays. At ZEPOSIA exposures higher than the recommended dosage without dose titration, first- and second-degree type 1 atrioventricular blocks were observed in healthy volunteers; however, in MS Study 1 and Study 2 and UC Study 1 and Study 3 with dose titration, Mobitz type 2 second- or third-degree atrioventricular blocks were not reported in patients treated with ZEPOSIA.

If treatment with ZEPOSIA is considered, advice from a cardiologist should be sought for those individuals:

- With significant QT prolongation (QTcF > 450 msec in males, > 470 msec in females)
- With arrhythmias requiring treatment with Class Ia or Class III anti-arrhythmic drugs
- With ischemic heart disease, heart failure, history of cardiac arrest or myocardial infarction, cerebrovascular disease, and uncontrolled hypertension
- With a history of with second-degree Mobitz type II or higher AV block, sick-sinus syndrome, or sinoatrial heart block [see Contraindications (4)]

5.4 Liver Injury

Clinically significant liver injury, including acute liver failure requiring transplant, has occurred in patients treated with ZEPOSIA in the postmarketing setting. Signs of liver injury, including elevated serum hepatic enzymes and elevated total bilirubin, have occurred as early as ten days after the first dose.

In MS Study 1 and Study 2, elevations of ALT to 5-fold the upper limit of normal (ULN) or greater occurred in 1.6% of patients treated with ZEPOSIA 0.92 mg and 1.3% of patients who received IFN beta-1a. Elevations of 3-fold the ULN or greater occurred in 5.5% of patients treated with ZEPOSIA and 3.1% of patients who received IFN beta-1a. The median time to an elevation of 3-fold the ULN was 6 months. The majority (79%) of patients continued treatment with ZEPOSIA with values returning to less than 3-fold the ULN within approximately 2-4 weeks. ZEPOSIA was discontinued for a confirmed elevation greater than 5-fold the ULN. Overall, the discontinuation rate because of elevations in hepatic enzymes was 1.1% of patients with MS treated with ZEPOSIA 0.92 mg and 0.8% of patients who received IFN beta-1a.

In UC Study 1, elevations of ALT to 5-fold the ULN or greater occurred in 0.9% of patients treated with ZEPOSIA 0.92 mg and 0.5% of patients who received placebo, and in UC Study 2 elevations occurred in 0.9% of patients and no patients, respectively. In UC Study 1, elevations of ALT to 3-fold the ULN or greater occurred in 2.6% of UC patients treated with ZEPOSIA 0.92 mg and 0.5% of patients who received placebo, and in UC Study 2 elevations occurred in 2.3% of patients and no patients, respectively. In controlled and uncontrolled UC studies, the majority (96%) of patients with ALT greater than 3-fold the ULN continued treatment with ZEPOSIA with values returning to less than 3-fold the ULN within approximately 2 to 4 weeks. Overall, the discontinuation rate because of elevations in hepatic enzymes was 0.4% in patients treated with ZEPOSIA 0.92 mg, and none in patients who received placebo in the controlled UC studies.

Individuals with an AST or ALT greater than 1.5-fold ULN were excluded from MS Study 1 and Study 2 and greater than 2 times the ULN for UC Study 1 and Study 3. There are no data to establish that patients with preexisting liver disease are at increased risk to develop elevated liver function test values when taking ZEPOSIA. Dosage adjustment in patients with mild or moderate hepatic impairment (Child-Pugh class A or B) is required [see Dosage and Administration (2.3)], and use of ZEPOSIA in patients with severe hepatic impairment (Child-Pugh class C) is not recommended [see Use in Specific Populations (8.6)].

Obtain transaminase and bilirubin levels, if not recently available (i.e., within 6 months), before initiation of ZEPOSIA. Obtain transaminase levels and total bilirubin levels periodically during treatment and until two months after ZEPOSIA discontinuation.

Patients should be monitored for signs and symptoms of any hepatic injury. Patients who develop symptoms suggestive of hepatic dysfunction, such as unexplained nausea, vomiting, abdominal pain, fatigue, anorexia, or jaundice and/or dark urine, should have hepatic enzymes promptly checked, and ZEPOSIA should be interrupted. Treatment should not be resumed if a plausible alternative etiology for the signs and symptoms cannot be established, because these patients are at risk for severe drug-induced liver injury.

5.5 Fetal Risk

There are no adequate and well-controlled studies in pregnant women. Based on animal studies, ZEPOSIA may cause fetal harm [see Use in Specific Populations (8.1)]. Because it takes approximately 3 months to eliminate ZEPOSIA from the body, women of childbearing potential should use effective contraception to avoid pregnancy during treatment and for 3 months after stopping ZEPOSIA [see Use in Specific Populations (8.3)].

5.6 Increased Blood Pressure

In MS Study 1 and Study 2, patients treated with ZEPOSIA had an average increase of approximately 1 to 2 mm Hg in systolic pressure over patients who received IFN beta-1a, and no effect on diastolic pressure. The increase in systolic pressure was first detected after approximately 3 months of treatment and persisted throughout treatment. Hypertension was reported as an adverse reaction in 3.9% of patients treated with ZEPOSIA 0.92 mg and in 2.1% of patients who received IFN beta-1a. Two patients treated with ZEPOSIA in MS Study 1 and one patient treated with interferon (IFN) beta-1a in Study 2 experienced a hypertensive crisis that was not clearly influenced by a concomitant medication.

The mean increase in systolic blood pressure (SBP) and diastolic blood pressure (DBP) in UC patients treated with ZEPOSIA is similar to patients with MS. In UC Study 1 and Study 3, the average increase from baseline in SBP was 3.7 mm Hg in patients treated with ZEPOSIA and 2.3 mm Hg in patients treated with placebo. In UC Study 2, the average increase from baseline in SBP was 5.1 mm Hg in patients treated with ZEPOSIA and 1.5 mm Hg in patients treated with placebo. There was no effect on DBP.

Hypertension was reported as an adverse reaction in 1.2% of patients treated with ZEPOSIA 0.92 mg and none in patients treated with placebo in UC Study 1 and Study 3, and in 2.2% and 2.2% of patients in UC Study 2, respectively. Hypertensive crisis was reported in two patients receiving ZEPOSIA and one patient receiving placebo.

Blood pressure should be monitored during treatment with ZEPOSIA and managed appropriately.

5.7 Respiratory Effects

Dose-dependent reductions in absolute forced expiratory volume over 1 second (FEV1) were observed in MS patients treated with ZEPOSIA as early as 3 months after treatment initiation. In the MS pooled analyses of Study 1 and Study 2, the decline in absolute FEV1 from baseline in patients treated with ZEPOSIA compared to patients who received IFN beta-1a was 60 mL (95% CI: -100, -20) at 12 months. The mean difference in percent predicted FEV1 at 12 months between patients treated with ZEPOSIA and patients who received IFN beta-1a was 1.9% (95% CI: -2.9, -0.8). Dose-dependent reductions in forced vital capacity (FVC) (absolute value and %-predicted) were also seen at Month 3 in pooled analyses comparing patients treated with ZEPOSIA to patients who received IFN beta-1a [60 mL, 95% CI (-110, -10); 1.4%, 95% CI: (-2.6, -0.2)], though significant reductions were not seen at other timepoints. There is insufficient information to determine the reversibility of the decrease in FEV1 or FVC after drug discontinuation. One patient in MS Study 1 discontinued ZEPOSIA because of dyspnea.

In UC Study 1 the mean difference in decline in absolute FEV1 from baseline in patients treated with ZEPOSIA compared to patients who received placebo was 22 mL (95% CI: -84, 39) at 10 weeks. The mean difference in percent predicted normal (PPN) FEV1 at 10 weeks between patients treated with ZEPOSIA compared to those who received placebo was 0.8% (95% CI: -2.6, 1.0). The difference in reductions in FVC (absolute value and %-predicted) seen at Week 10 in UC Study 1, comparing patients who were treated with ZEPOSIA to those who received placebo was 44 mL, 95% CI (-114, 26); 0.5%, 95% CI (-2.3, 1.2), respectively. There is insufficient information to determine the reversibility of observed decreases in FEV1 or FVC after discontinuation of ZEPOSIA, or whether changes could be progressive with continued use.

Spirometric evaluation of respiratory function should be performed during therapy with ZEPOSIA, if clinically indicated.

5.8 Macular Edema

S1P receptor modulators, including ZEPOSIA, have been associated with an increased risk of macular edema. Obtain a baseline evaluation of the fundus, including the macula, near the start of treatment with ZEPOSIA. Perform an examination of the fundus, including the macula, periodically while on therapy and any time there is a change in vision.

In MS Study 1 and Study 2, macular edema was observed in 0.3% of patients treated with ZEPOSIA and in 0.3% of patients who received IFN beta-1a. Macular edema was reported in a total of 1 (0.2%) patient in UC Study 1 and Study 3, and in 1 (0.4%) patient in UC Study 2 treated with ZEPOSIA, and in no patients who received placebo.

Continuation of ZEPOSIA therapy in patients with macular edema has not been evaluated. Macular edema over an extended period of time (i.e., 6 months) can lead to permanent visual loss. Consider discontinuing ZEPOSIA if macular edema develops; this decision should include an assessment of the potential benefits and risks for the individual patient. The risk of recurrence after rechallenge has not been evaluated.

Macular Edema in Patients with a History of Uveitis or Diabetes Mellitus

Patients with a history of uveitis and patients with a history of diabetes mellitus are at increased risk of macular edema during ZEPOSIA therapy.

5.9 Cutaneous Malignancies

The risk of cutaneous malignancies (including basal cell carcinoma (BCC), squamous cell carcinoma (SCC), and melanoma) is increased in patients treated with S1P receptor modulators. Cases of BCC, SCC, and melanoma have been reported in patients treated with ZEPOSIA; melanoma and BCC were reported in controlled trials [see Adverse Reactions (6.1)]. Kaposi’s sarcoma and Merkel cell carcinoma have also been reported in patients treated with S1P receptor modulators in the postmarketing setting.

Skin examinations are recommended prior to or shortly after the start of treatment and periodically thereafter for all patients, particularly those with risk factors for skin cancer. Providers and patients are advised to monitor for suspicious skin lesions. If a suspicious skin lesion is observed, it should be promptly evaluated. As usual for patients with increased risk for skin cancer, exposure to sunlight and ultraviolet light should be limited by wearing protective clothing and using a sunscreen with a high protection factor. Concomitant phototherapy with UV-B radiation or PUVA photochemotherapy is not recommended in patients taking ZEPOSIA.

5.10 Posterior Reversible Encephalopathy Syndrome

Rare cases of posterior reversible encephalopathy syndrome (PRES) have been reported in patients receiving a S1P receptor modulator. In MS controlled clinical trials with ZEPOSIA, one case of PRES was reported. Should a ZEPOSIA-treated patient develop any unexpected neurological or psychiatric symptoms/signs (e.g., cognitive deficits, behavioral changes, cortical visual disturbances, or any other neurological cortical symptoms/signs), any symptom/sign suggestive of an increase of intracranial pressure, or accelerated neurological deterioration, the physician should promptly schedule a complete physical and neurological examination and should consider an MRI. Symptoms of PRES are usually reversible but may evolve into ischemic stroke or cerebral hemorrhage. Delay in diagnosis and treatment may lead to permanent neurological sequelae. If PRES is suspected, treatment with ZEPOSIA should be discontinued.

5.11 Unintended Additive Immunosuppressive Effects from Prior Treatment with Immunosuppressive or Immune-Modulating Drugs

When switching from drugs with prolonged immune effects, the half-life and mode of action of these drugs must be considered to avoid unintended additive immunosuppressive effects while at the same time minimizing risk of disease reactivation, when initiating ZEPOSIA.

Initiating treatment with ZEPOSIA after treatment with alemtuzumab is not recommended [see Drug Interactions (7)].

5.12 Severe Increase in Multiple Sclerosis Disability after Stopping ZEPOSIA

In MS, severe exacerbation of disease, including disease rebound, has been rarely reported after discontinuation of a S1P receptor modulator. The possibility of severe exacerbation of disease should be considered after stopping ZEPOSIA treatment. Patients should be observed for a severe increase in disability upon ZEPOSIA discontinuation and appropriate treatment should be instituted, as required.

After stopping ZEPOSIA in the setting of PML, monitor for development of immune reconstitution inflammatory syndrome (PML-IRIS) [see Warnings and Precautions (5.2)].

5.13 Immune System Effects after Stopping ZEPOSIA

After discontinuing ZEPOSIA, the median time for peripheral blood lymphocytes to return to the normal range was approximately 30 days, with approximately 80% to 90% of patients in the normal range within 3 months [see Clinical Pharmacology (12.2)]. Use of immunosuppressants within this period may lead to an additive effect on the immune system, and therefore caution should be applied when initiating other drugs 4 weeks after the last dose of ZEPOSIA [see Drug Interactions (7)].

6 ADVERSE REACTIONS

The following serious adverse reactions are described elsewhere in the labeling:

- Infections [see Warnings and Precautions (5.1)]
- Progressive Multifocal Leukoencephalopathy [see Warnings and Precautions (5.2)]
- Bradyarrhythmia and Atrioventricular Conduction Delays [see Warnings and Precautions (5.3)]
- Liver Injury [see Warnings and Precautions (5.4)]
- Fetal Risk [see Warnings and Precautions (5.5)]
- Increased Blood Pressure [see Warnings and Precautions (5.6)]
- Respiratory Effects [see Warnings and Precautions (5.7)]
- Macular Edema [see Warnings and Precautions (5.8)]
- Cutaneous Malignancies [see Warnings and Precautions (5.9)]
- Posterior Reversible Encephalopathy Syndrome [see Warnings and Precautions (5.10)]
- Unintended Additive Immunosuppressive Effects from Prior Treatment with Immunosuppressive or Immune-Modulating Drugs [see Warnings and Precautions (5.11)]
- Severe Increase in Multiple Sclerosis Disability after Stopping ZEPOSIA [see Warnings and Precautions (5.12)]
- Immune System Effects after Stopping ZEPOSIA [see Warnings and Precautions (5.13)]

6.1 Clinical Trials Experience

Because clinical trials are conducted under widely varying conditions, adverse reaction rates observed in the clinical trials of a drug cannot be directly compared to rates in the clinical trials of another drug and may not reflect the rates observed in clinical practice.

Common Adverse Reactions

Multiple Sclerosis

The safety of ZEPOSIA was evaluated in two randomized, double-blind, active comparator-controlled clinical studies (MS Study 1 and MS Study 2) in which 882 patients received ZEPOSIA 0.92 mg [see Clinical Studies (14.1)].

Table 2 lists adverse reactions that occurred in at least 2% of ZEPOSIA-treated patients and greater than comparator. The most common adverse reactions that occurred in at least 4% of ZEPOSIA-treated patients and greater than in patients who received IFN beta-1a were upper respiratory infection, hepatic transaminase elevation, orthostatic hypotension, urinary tract infection, back pain, and hypertension.

Table 2: Adverse Reactions with an Incidence of at Least 2% in ZEPOSIA-Treated Patients and at Least 1% Greater than IFN beta-1a in Patients with Multiple Sclerosis (Pooled MS Study 1 and Study 2)a
Adverse Reactions | MS Studies 1 and 2
Adverse Reactions | ZEPOSIA 0.92 mg Once Dailye (n=882) % | IFN beta-1a 30 mcg Intramuscularly Once Weekly (n=885) %
Upper respiratory infectionb | 26 | 23
Hepatic transaminase elevationc | 10 | 5
Orthostatic hypotension | 4 | 3
Urinary tract infection | 4 | 3
Back pain | 4 | 3
Hypertensiond | 4 | 2
Upper abdominal pain | 2 | 1
a Data are not an adequate basis for comparison of rates between ZEPOSIA and the active control.
b Includes the following terms: nasopharyngitis, upper respiratory tract infection, pharyngitis, respiratory tract infection, bronchitis, rhinitis, viral respiratory tract infection, viral upper respiratory tract infection, rhinorrhea, tracheitis, and laryngitis.
c Includes the following terms: alanine aminotransferase increased, gamma-glutamyl transferase increased, aspartate aminotransferase increased, hepatic enzyme increased, abnormal liver function test, and increased transaminases.
d Includes hypertension, essential hypertension, and orthostatic hypertension.
e ZEPOSIA was initiated with a 7-day titration [see Dosage and Administration (2.2)].

Ulcerative Colitis

The safety of ZEPOSIA was evaluated in two randomized, double-blind, placebo-controlled clinical studies [UC Study 1 (induction), n=429; and UC Study 2 (maintenance), n=230] in adult patients with moderately to severely active ulcerative colitis [see Clinical Studies (14.2)]. Additional data from the induction period of a randomized, double-blind, placebo-controlled study (UC Study 3, NCT01647516) included 67 patients who received ZEPOSIA 0.92 mg once daily.

Common adverse reactions in UC Study 1 and Study 3 and in UC Study 2 are listed in Tables 3 and 4, respectively. The most common adverse reactions that occurred in at least 4% of ZEPOSIA-treated patients and greater than in patients who received placebo were liver test increased, upper respiratory infection, and headache.

Table 3: Adverse Reactions with an Incidence of at Least 2% in ZEPOSIA-Treated Patients and at Least 1% Greater than Placebo in Patients with Ulcerative Colitis (Pooled UC Study 1 and Study 3)
Adverse Reactions | Induction Periods (UC Study 1 and Study 3)
Adverse Reactions | ZEPOSIA 0.92 mg Once Daily (n=496)c,d % | Placebo (n=281) %d
Upper respiratory infectiona | 5 | 4
Liver test increasedb | 5 | 0
Headache | 4 | 3
Pyrexia | 3 | 2
Nausea | 3 | 2
Arthralgia | 3 | 1
a Includes the following terms: streptococcal pharyngitis, pharyngotonsillitis, bacterial pharyngitis, nasopharyngitis, upper respiratory tract infection, pharyngitis, sinusitis, tonsillitis, viral upper respiratory tract infection, laryngitis, acute sinusitis, catarrh, chronic sinusitis, upper respiratory tract inflammation, chronic tonsillitis, viral pharyngitis, viral sinusitis, bacterial sinusitis, bacterial upper respiratory tract infection, viral labyrinthitis, laryngeal inflammation, and pharyngeal inflammation.
b Includes the following terms: gamma-glutamyl transferase increased, alanine aminotransferase increased, aspartate aminotransferase increased, hepatic enzyme increased, hyperbilirubinemia, liver function test increased, blood alkaline phosphatase increased, and increased transaminases.
c ZEPOSIA was initiated with a 7-day titration [see Dosage and Administration (2.2)].
d Percentages were calculated as the sum of each individual study percentage multiplied by its Cochran-Mantel-Haenszel weight.

Table 4: Adverse Reactions with an Incidence of at Least 4% in ZEPOSIA-Treated Patients and at Least 1% Greater than Placebo in Patients with Ulcerative Colitis (UC Study 2)
Adverse Reactions | Maintenance Period (UC Study 2)
Adverse Reactions | ZEPOSIA 0.92 mg Once Daily (n=230) % | Placebo (n=227) %
Liver test increaseda | 11 | 2
Headache | 5 | <1
a Includes the following terms: gamma-glutamyl transferase increased, alanine aminotransferase increased, aspartate aminotransferase increased, hepatic enzyme increased, hyperbilirubinemia, blood bilirubin increased, liver function test increased, and blood alkaline phosphatase increased.

Other Adverse Reactions

Reduction in Heart Rate

Initiation of ZEPOSIA may result in transient decrease in heart rate in MS and UC patients [see Warnings and Precautions (5.3)].

Respiratory Effects

Dose-dependent reductions in absolute FEV1 and FVC were observed in MS and UC patients treated with ZEPOSIA [see Warnings and Precautions (5.7)].

Malignancies

Malignancies, such as melanoma, basal cell carcinoma, breast cancer, seminoma, cervical carcinoma, and adenocarcinomas, including rectal adenocarcinoma, were reported with ZEPOSIA in controlled trials of MS and UC. An increased risk of cutaneous malignancies has been reported with S1P receptor modulators [see Warnings and Precautions (5.9)].

Hypersensitivity

Hypersensitivity, including rash and urticaria, has been reported with ZEPOSIA in active-controlled MS clinical trials.

Peripheral Edema

Peripheral edema was observed in 3% of ZEPOSIA-treated patients and in 0.4% of patients who received placebo in UC Study 2.

6.2 Postmarketing Experience

The following adverse reactions have been identified during postapproval use of ZEPOSIA. Because these reactions are reported voluntarily from a population of uncertain size, it is not always possible to reliably estimate their frequency or establish a causal relationship to drug exposure.

Hepatobiliary Disorders: Liver injury [see Warnings and Precautions (5.4)]

7 DRUG INTERACTIONS

Tables 5 and 6 include drugs with clinically important drug and vaccine interactions when administered concomitantly with ZEPOSIA and instructions for preventing or managing them.

Table 5: Clinically Relevant Interactions Affecting Drugs and Vaccines Co-administered with ZEPOSIA
Anti-Neoplastic, Immune-Modulating, or Non-Corticosteroid Immunosuppressive Therapies
Clinical Impact: | ZEPOSIA has not been studied in combination with anti-neoplastic, immune-modulating, or non-corticosteroid immunosuppressive therapies with the exception of cyclosporine, which had no pharmacokinetic interaction [see Clinical Pharmacology (12.3)].
Prevention or Management: | Caution should be used during concomitant administration because of the risk of additive immune effects during such therapy and in the weeks following administration [see Warnings and Precautions (5.1)]. When switching from drugs with prolonged immune effects, the half-life and mode of action of these drugs must be considered in order to avoid unintended additive immunosuppressive effects [see Warnings and Precautions (5.11)]. Alemtuzumab: Initiating treatment with ZEPOSIA after alemtuzumab is not recommended because of the characteristics and duration of alemtuzumab immune suppressive effects. Beta interferon or glatiramer acetate: ZEPOSIA can generally be started immediately after discontinuation of beta interferon or glatiramer acetate.
Anti-Arrhythmic Drugs, QT Prolonging Drugs, Drugs That May Decrease Heart Rate
Clinical Impact: | ZEPOSIA has not been studied in patients taking QT prolonging drugs. Class Ia (e.g., quinidine, procainamide) and Class III (e.g., amiodarone, sotalol) anti-arrhythmic drugs have been associated with cases of Torsades de Pointes in patients with bradycardia.
Prevention or Management: | If treatment with ZEPOSIA is considered in patients on Class Ia or Class III anti-arrhythmic drugs, advice from a cardiologist should be sought [see Warnings and Precautions (5.3)]. Because of the potential additive effects on heart rate, treatment with ZEPOSIA should generally not be initiated in patients who are concurrently treated with QT prolonging drugs with known arrhythmogenic properties [see Warnings and Precautions (5.3)]. If treatment initiation with ZEPOSIA is considered in patients on QT prolonging drugs, advice from a cardiologist should be sought.
Combination Beta Blocker and Calcium Channel Blocker
Clinical Impact: | The co-administration of ZEPOSIA with both a beta blocker and a calcium channel blocker has not been studied. However, there is a potential of additive effects on heart rate.
Prevention or Management: | Treatment with ZEPOSIA should generally not be initiated in patients who are concurrently treated with both a heart rate lowering calcium channel blocker (e.g., verapamil, diltiazem) and beta blocker [see Warnings and Precautions (5.3)]. If treatment initiation with ZEPOSIA is considered in patients on both a heart rate lowering calcium channel blocker and beta blocker, advice from a cardiologist should be sought.
Vaccination
Clinical Impact: | During, and for up to three months after, discontinuation of treatment with ZEPOSIA, vaccinations may be less effective. The use of live attenuated vaccines may carry the risk of infection.
Prevention or Management: | Live attenuated vaccines should be avoided during ZEPOSIA treatment and for up to 3 months after discontinuation of treatment with ZEPOSIA [see Warnings and Precautions (5.1)].

Table 6: Clinically Relevant Interactions Affecting ZEPOSIA When Co-administered with Other Drugs
Monoamine Oxidase (MAO) Inhibitors
Clinical Impact: | The effect of MAO inhibition on ozanimod and/or its metabolites has not been studied clinically. Potential effects on efficacy or safety with co-administration of MAO inhibitors because of altered exposures of ozanimod and/or its metabolites cannot be ruled out.
Prevention or Management: | Co-administration of ZEPOSIA with MAO inhibitors (e.g., selegiline, phenelzine, linezolid) is contraindicated. At least 14 days should elapse between discontinuation of ZEPOSIA and initiation of treatment with MAO inhibitors.
Strong CYP2C8 Inhibitors
Clinical Impact: | Co-administration of ZEPOSIA with strong CYP2C8 inhibitors increases the exposure of the active metabolites of ozanimod [see Clinical Pharmacology (12.3)], which may increase the risk of ZEPOSIA adverse reactions.
Prevention or Management: | Co-administration of ZEPOSIA with strong CYP2C8 inhibitors (e.g., gemfibrozil) is not recommended.
Strong CYP2C8 Inducers
Clinical Impact: | Co-administration of ZEPOSIA with strong CYP2C8 inducers (e.g., rifampin) reduces the exposure of the major active metabolites of ozanimod [see Clinical Pharmacology (12.3)], which may decrease the efficacy of ZEPOSIA.
Prevention or Management: | Co-administration of ZEPOSIA with strong CYP2C8 inducers should be avoided.

8 USE IN SPECIFIC POPULATIONS

8.1 Pregnancy

Pregnancy Exposure Registry

There is a pregnancy exposure registry that monitors pregnancy outcomes in women exposed to ZEPOSIA during pregnancy. Healthcare providers are encouraged to register patients on-line, or pregnant women may register themselves at https://www.zeposiapregnancyregistry.com/or by calling 1-877-301-9314. Currently this registry is enrolling women with MS. Information regarding registration of pregnant women with UC will be made available in the future.

Risk Summary

There are no adequate data on the developmental risk associated with the use of ZEPOSIA in pregnant women. In animal studies, administration of ozanimod during pregnancy produced adverse effects on development, including embryolethality, an increase in fetal malformations, and neurobehavioral changes, in the absence of maternal toxicity. In rabbits, fetal blood vessel malformations occurred at clinically relevant maternal ozanimod and metabolite exposures (see Data). The receptor affected by ozanimod (sphingosine1-phosphate) has been demonstrated to have an important role in embryogenesis, including vascular and neural development.

In the U.S. general population, the estimated background risk of major birth defects and miscarriage in clinically recognized pregnancies is 2% to 4% and 15% to 20%, respectively. The background risk of major birth defects and miscarriage for the indicated population is unknown.

Data

Animal Data

Oral administration of ozanimod (0, 0.2, 1, or 5 mg/kg/day) to female rats during organogenesis resulted in a marked increase in embryofetal mortality, increased fetal malformations and skeletal variations (abnormal/delayed ossification), and reduced fetal body weight at the highest dose tested. No maternal toxicity was observed. At the no-effect dose (1 mg/kg/day) for adverse effects on embryofetal development, plasma ozanimod exposure (AUC) for ozanimod was approximately 60 times that in humans at the maximum recommended human dose (MRHD) of 0.92 mg/day. Plasma AUCs for major human metabolites, CC112273 and CC1084037, were similar to and less than, respectively, those in humans at the MRHD.

Oral administration of ozanimod (0, 0.2, 0.6, or 2.0 mg/kg/day) to female rabbits during organogenesis resulted in a marked increase in embryofetal mortality at the highest dose tested and increased fetal malformations (malformed blood vessels) and skeletal variations at the mid and high doses. Maternal toxicity was not observed. At the no-effect dose (0.2 mg/kg/day) for adverse effects on embryofetal development in rabbit, plasma ozanimod exposure (AUC) was approximately 2 times that in humans at the MRHD; plasma AUCs for major human metabolites, CC112273 and CC1084037, were less than those in humans at the MRHD.

Oral administration of ozanimod (0, 0.2, 0.7, or 2 mg/kg/day) to female rats throughout gestation and lactation resulted in persistent body weight reductions and long-term effects on reproductive (prolonged estrus cycle) and neurobehavioral (increased motor activity) function in offspring at the highest dose tested, which was not associated with maternal toxicity. At the no-effect dose (0.7 mg/kg/day) for adverse effects on pre- and postnatal development, plasma ozanimod exposure (AUC) was 30 times that in humans at the MRHD; plasma AUCs for major human metabolites, CC112273 and CC1084037, were less than those in humans at the MRHD.

8.2 Lactation

Risk Summary

There are no data on the presence of ozanimod in human milk, the effects on the breastfed infant, or the effects of the drug on milk production. Following oral administration of ozanimod, ozanimod and/or metabolites were detected in the milk of lactating rat at levels higher than those in maternal plasma.

The developmental and health benefits of breastfeeding should be considered along with the mother's clinical need for ZEPOSIA and any potential adverse effects on the breastfed infant from ZEPOSIA or from the underlying maternal condition.

8.3 Females and Males of Reproductive Potential

Contraception

Before initiation of ZEPOSIA treatment, women of childbearing potential should be counseled on the potential for a serious risk to the fetus and the need for contraception during treatment with ZEPOSIA [see Use in Specific Populations (8.1)]. Because of the time it takes to eliminate the drug from the body after stopping treatment, the potential risk to the fetus may persist and women of childbearing age should also use effective contraception for 3 months after stopping ZEPOSIA.

8.4 Pediatric Use

Safety and effectiveness in pediatric patients have not been established.

8.5 Geriatric Use

Clinical studies of ZEPOSIA did not include sufficient numbers of subjects aged 65 and over to determine whether they respond differently from younger subjects. No clinically significant differences in the pharmacokinetics of ozanimod and CC112273 were observed based on age [see Clinical Pharmacology (12.3)]. Monitor elderly patients for cardiac and hepatic adverse reactions, because of the greater frequency of reduced cardiac and hepatic function in the elderly population.

8.6 Hepatic Impairment

In patients with mild (Child-Pugh class A) or moderate hepatic impairment (Child-Pugh class B), the exposures of ozanimod and its active metabolites are higher than those in healthy controls [see Clinical Pharmacology (12.3)], which may increase the risk of adverse reactions. Therefore, dosage adjustment in patients with mild or moderate hepatic impairment is required [see Dosage and Administration (2.3)].

The pharmacokinetics of ozanimod and its active metabolites were not evaluated in patients with severe hepatic impairment (Child-Pugh class C). Therefore, use of ZEPOSIA in patients with severe hepatic impairment is not recommended.

11 DESCRIPTION

ZEPOSIA contains ozanimod, a sphingosine 1-phosphate receptor modulator and is supplied as ozanimod hydrochloride (HCl).

The chemical name of ozanimod HCl is 5-(3-{(1S)-1-[(2-hydroxyethyl)amino]-2,3-dihydro-1H-inden-4-yl}-1,2,4-oxadiazol-5-yl)-2-[(propan-2-yl)oxy]benzonitrile, monohydrochloride.

Ozanimod HCl is a white to off-white solid that is freely soluble in water and alcohol with a molecular weight of 440.92 g/mol.

The chemical structure is:

ZEPOSIA capsules are provided as hard gelatin capsules for oral administration, containing 0.23, 0.46, or 0.92 mg of ozanimod (equivalent to 0.25, 0.5, and 1 mg ozanimod HCl, respectively). ZEPOSIA capsules consist of the following inactive ingredients: colloidal silicon dioxide, croscarmellose sodium, magnesium stearate, and microcrystalline cellulose. The capsule shell, imprinted with black ink, contains the following inactive ingredients: black iron oxide, gelatin, red iron oxide, titanium dioxide, and yellow iron oxide.

12 CLINICAL PHARMACOLOGY

12.1 Mechanism of Action

Ozanimod is a sphingosine 1-phosphate (S1P) receptor modulator that binds with high affinity to S1P receptors 1 and 5. Ozanimod blocks the capacity of lymphocytes to egress from lymph nodes, reducing the number of lymphocytes in peripheral blood. Ozanimod has minimal or no activity on S1P2, S1P3, and S1P4. The mechanism by which ozanimod exerts therapeutic effects in multiple sclerosis and ulcerative colitis is unknown but may involve the reduction of lymphocyte migration into the central nervous system and intestine.

12.2 Pharmacodynamics

Reduction in Blood Lymphocyte Counts

In active-controlled MS and controlled UC clinical trials, mean lymphocyte counts decreased to approximately 45% of baseline at 3 months (approximate mean blood lymphocyte counts 0.8 × 10^9/L), and low lymphocyte counts were maintained during treatment with ZEPOSIA [see Warnings and Precautions (5.1)].

After discontinuing ZEPOSIA 0.92 mg, the median time for peripheral blood lymphocytes to return to the normal range was 30 days, with approximately 90% of patients in the normal range within 3 months.

Reduction in Heart Rate

ZEPOSIA may cause a transient decrease in heart rate on initiation of dosing [see Warnings and Precautions (5.3)]. An up-titration schedule of ZEPOSIA 0.23 mg followed by doses of 0.46 mg, and 0.92 mg attenuates the magnitude of heart rate reductions [see Dosage and Administration (2.2)].

Tyramine Challenge Test

No clinically significant effect in tyramine induced pressor response was observed when steady state ZEPOSIA 0.92 mg (recommended dose) or 1.84 mg was co-administered with increasing doses of oral tyramine (a monoamine oxidase substrate).

Drug Interaction Studies

Sympathomimetic Agents

No clinically significant differences in heart rate or blood pressure was observed when ZEPOSIA 1.84 mg daily (two times the recommended dosage) for 28 days was co-administered with a single dose of 60 mg pseudoephedrine (a sympathomimetic agent) compared to pseudoephedrine alone.

Beta Blocker or Calcium Channel Blocker

The effect of co-administration of the maintenance dosage of ZEPOSIA, propranolol, or diltiazem, or administration with both a beta blocker and a calcium channel blocker taken together has not been studied [see Drug Interactions (7)].

Pulmonary Function

Dose-dependent reductions in FEV1 and FVC were observed in patients treated with ZEPOSIA [see Warnings and Precautions (5.7)].

Cardiac Electrophysiology

Following a 14-day titration regimen of once daily doses of ozanimod 0.23 mg for 4 days, 0.46 mg for 3 days, 0.92 mg for 3 days, and 1.84 mg (2 times the maximum approved recommended dose) for 4 days in healthy subjects, ZEPOSIA did not prolong the QTc interval to any clinically relevant extent [see Warnings and Precautions (5.3)].

12.3 Pharmacokinetics

The steady state exposure parameters of ozanimod and its major active metabolite, CC112273 are summarized in Table 7. Population pharmacokinetic analysis indicated no meaningful differences in these pharmacokinetic parameters in patients with relapsing MS or UC.

Table 7: Exposure Parameters of Ozanimod and its Major Metabolitea
Parameters | Ozanimod | CC112273
Cmax,ss | 0.244 ng/mL (31.8%) | 6.98 ng/mL (42.7%)
AUCtau,ss | 4.46 ng*h/mL (31.8%) | 143.77 ng*h/mL (39.2%)
Dose Proportionality | The Cmax and AUC increases proportionally over the ozanimod dose range from 0.46 mg to 0.92 mg.
Time to Steady State | 102 hours (28.2%)b | 45 days (45%)
Accumulation Ratio | 2.40 (21.1%) b | 16 (101%)
a Mean [coefficient of variation (CV%)] following ozanimod 0.92 mg once daily dose in relapsing MS patients, unless otherwise specified.
b In healthy subjects.
Cmax,ss = maximum observed plasma concentration at steady state, AUCtau,ss = area under the plasma concentration-time curve during a dosage interval at steady state.

Absorption

The Tmax of ozanimod is approximately 6 to 8 hours.

Effect of Food

No clinically significant differences in the Cmax and AUC of ozanimod were observed following administration of ZEPOSIA with either a high-fat, high-calorie meal (1000 calories, 50% fat) or a low-fat, low-calorie meal (300 calories, 10% fat) compared to fasted conditions [see Dosage and Administration (2.2)].

Distribution

The mean (CV%) apparent volume of distribution of ozanimod (Vz/F) is 5590 L (27%). Human plasma proteins binding of ozanimod, CC112273 and CC1084037 is approximately 98.2%, 99.8%, and 99.3%, respectively.

Elimination

The mean (CV%) plasma half-life (t1/2) of ozanimod is approximately 21 hours (15%). The mean (CV%) effective half-life (t1/2) of CC112273 and its direct interconverting metabolite CC1084037 was approximately 11 days (104%) in relapsing MS patients. The mean (CV%) apparent oral clearance for ozanimod was approximately 192 L/h (37%).

Metabolism

Ozanimod is metabolized by multiple enzymes to form circulating major active metabolites (e.g., CC112273 and CC1084037) and minor active metabolites (e.g., RP101988, RP101075, and RP112509) with similar activity and selectivity for S1P1 and S1P5. Ozanimod is metabolized by ALDH/ADH to form carboxylate metabolite RP101988 and by CYP3A4 to form RP101075. RP101075 is then metabolized either by NAT-2 to form a minor active metabolite RP101442 or by MAO-B to form CC112273. CC112273 is then metabolized by CYP2C8 to form RP112509 or reduced to form CC1084037. CC1084037 is metabolized by AKR 1C1/1C2 and/or 3β- and 11β-HSD to form CC112273. The interconversion between CC112273 and CC1084037 favors CC112273. Approximately 94% of circulating total active drug exposure is represented by ozanimod (6%), CC112273 (73%), and CC1084037 (15%), in humans.

Excretion

Following a single oral dose of radiolabeled ozanimod 0.92 mg, approximately 26% of the radioactivity was recovered in urine and 37% in feces, primarily composed of inactive metabolites.

Specific Populations

Geriatric Patients

Population pharmacokinetic analyses showed that steady state exposure (AUC) of CC112273 in UC patients over 65 years of age was approximately 3% to 4% greater than patients 45 to 65 years of age and 27% greater than adult patients under 45 years of age. There is no meaningful difference in the pharmacokinetics in elderly patients with UC [see Use in Specific Populations (8.5)].

Male and Female Patients

No clinically significant differences in the pharmacokinetics of ozanimod and CC112273 were observed based on sex or weight.

Racial or Ethnic Groups

In a dedicated Japanese PK bridging study, following repeated dosing of 0.96 mg ZEPOSIA, ozanimod exposures (Cmax and AUCtau) were unchanged and CC112273 exposures (Cmax and AUCtau) were approximately 28% and 43% higher, respectively, in Japanese subjects (N=10) compared to Caucasian subjects (N=12). These differences are not considered clinically meaningful.

Patients with Renal Impairment

In a dedicated renal impairment trial, following a single oral dose of 0.23 mg ZEPOSIA, exposures (AUClast) for ozanimod and CC112273 were approximately 27% higher and 23% lower, respectively, in subjects with end stage renal disease (N=8) compared to subjects with normal renal function (N=8). Based on this trial, renal impairment has no clinically important effects on pharmacokinetics of ozanimod or CC112273.

Patients with Hepatic Impairment

In a hepatic impairment study, following an 8-day titration regimen of once daily doses of ZEPOSIA 0.23 mg on days 1 to 4, 0.46 mg on days 5 to 7, and 0.92 mg on day 8, in subjects with mild hepatic impairment (Child-Pugh class A, N=8), mean exposures (AUClast) of ozanimod and active metabolites CC112273 and CC1084037 on day 8 increased by 60%, 98%, and 107%, respectively, compared to healthy controls (N=8). In subjects with moderate hepatic impairment (Child-Pugh class B, N=8) mean exposures (AUClast) of ozanimod and active metabolites CC112273 and CC1084037 on day 8 increased by 17%, 38%, and 61%, respectively, compared to healthy controls.

The pharmacokinetics of ozanimod or its active metabolites were not evaluated in patients with severe hepatic impairment (Child-Pugh class C) [see Use in Specific Populations (8.6)].

Smokers

Population PK analyses showed that CC112273 steady-state exposure (AUC) was approximately 50% lower in smokers than in nonsmokers, although for smokers this reduction in exposure did not result in meaningful differences in absolute lymphocyte count (ALC) reduction or an apparent impact on clinical efficacy.

Drug Interaction Studies

Clinical/In Vivo Studies

Strong CYP3A and P-gp Inhibitors

No clinically significant differences in the pharmacokinetics of ozanimod and its major active metabolites CC112273 and CC1084037 were observed when co-administered with itraconazole (P-gp and strong CYP3A inhibitor).

Strong CYP2C8 Inhibitors

Co-administration of ozanimod with gemfibrozil (a strong CYP2C8 inhibitor) increased exposure (AUC) of active metabolites CC112273 and CC1084037 by approximately 47% and 69%, respectively, with no change in the AUC of ozanimod [see Drug Interactions (7)].

BCRP Inhibitors

Co-administration of ozanimod with cyclosporine (BCRP inhibitor) had no effect on the exposure of ozanimod or the major active metabolites CC112273 and CC1084037.

Strong CYP2C8 Inducers

Co-administration of rifampin (a strong inducer of CYP3A and P-gp, and a moderate inducer of CYP2C8) 600 mg once daily at steady state and a single dose of ZEPOSIA 0.92 mg reduced the exposure (AUC) for ozanimod, CC112273, and CC1084037 by approximately 24%, 60%, and 55%, respectively. The effect on CC112273 and CC1084037 is primarily caused by induction of CYP2C8 [see Drug Interactions (7)].

Prednisone and Prednisolone

Population pharmacokinetic analyses showed that concomitant administration of prednisone or prednisolone in patients with UC did not alter the apparent clearance of the predominant active metabolite CC112273. The impact of prednisone or prednisolone on the pharmacokinetics of CC1084037 is unknown.

Monoamine Oxidase Inhibitors

No clinical studies evaluating the drug interaction potential of ozanimod with MAO inhibitors have been conducted [see Drug Interactions (7)].

Monoamine Oxidase Substrates

Co-administration of steady state 0.92 mg or 1.84 mg ozanimod had no effect on the plasma concentrations of oral tyramine, an MAO substrate.

Oral Contraceptives

No clinically significant differences in the pharmacokinetic of oral contraceptive containing ethinyl estradiol and norethindrone were observed when co-administered with ozanimod.

In Vitro Studies

Cytochrome P450 (CYP) Enzymes

Ozanimod, CC112273, CC1084037, and other metabolites do not inhibit CYPs 1A2, 2B6, 2C19, 2C8, 2C9, 2D6, and 3A, and do not induce CYPs 1A2, 2B6, and 3A.

In vitro, CC112273 and CC1084037 inhibited MAO-B (IC50 values of 5.72 nM and 58 nM, respectively) with more than 1000-fold selectivity over monoamine oxidase A (MAO-A) [see Drug Interactions (7)].

Transporter Systems

Ozanimod, CC112273, CC1084037, and other metabolites do not inhibit P-gp, OATP1B1, OATP1B3, OAT1, OAT3, MATE1, or MATE2-K. CC112273 and CC1084037 do not inhibit BCRP at clinically relevant concentrations.

13 NONCLINICAL TOXICOLOGY

13.1 Carcinogenesis, Mutagenesis, Impairment of Fertility

Carcinogenesis

Oral administration of ozanimod (0, 8, 25, or 80 mg/kg/day) to Tg.rasH2 mice for 26-weeks resulted in an increase in hemangioma and hemangiosarcoma (combined) in males and females at the mid and high doses tested.

Oral administration of ozanimod (0, 0.2, 0.7, or 2 mg/kg/day) to rats for 2 years resulted in no increase in tumors. At the highest dose tested (2 mg/kg/day), plasma exposure (AUC) for ozanimod was approximately 100 times that in humans at the maximum recommended human dose (MRHD) of 0.92 mg/day. Plasma AUCs for major human metabolites, CC112273 and CC1084037, were similar to and less than, respectively, those in humans at the MRHD.

Mutagenesis

Ozanimod was negative in a battery of in vitro (Ames, mouse lymphoma tk) and in vivo (rat micronucleus) assays. Metabolite CC112273 was negative in in vitro (Ames, chromosomal aberration in mammalian cell) assays. Metabolite CC1084037 was negative in an Ames assay, and positive in an in vitro chromosomal aberration assay in human (TK6) cells but negative in an in vivo rat micronucleus/comet assay.

Impairment of Fertility

Oral administration of ozanimod (0, 0.2, 2, or 30 mg/kg/day) to male and female rats prior to and during mating and continuing through gestation day 7 resulted in no adverse effects on fertility. At the highest dose tested (30 mg/kg/day), plasma ozanimod exposure (AUC) was approximately 1600 times that in humans at the maximum recommended human dose (MRHD) (0.92 mg/day); plasma AUCs for metabolites, CC112273 and CC1084037, at 30 mg/kg/day were 13 and 3 times, respectively, those in humans at the MRHD.

14 CLINICAL STUDIES

14.1 Multiple Sclerosis

The efficacy of ZEPOSIA was demonstrated in 2 randomized, double-blind, double-dummy, parallel-group, active comparator-controlled clinical trials of similar design, in patients with relapsing forms of MS [MS Study 1 (NCT02294058) and MS Study 2 (NCT02047734)]. Patients in Study 1 were treated until the last enrolled patient completed 1 year of treatment. Patients in Study 2 were treated for 24 months. Both studies included patients who had experienced at least 1 relapse within the prior year, or 1 relapse within the prior 2 years with evidence of at least a gadolinium-enhancing (GdE) lesion in the prior year, and had an Expanded Disability Status Scale (EDSS) score from 0 to 5.0 at baseline. Patients with primary progressive MS were excluded.

Patients were randomized to receive either ZEPOSIA 0.92 mg given orally once daily, beginning with a dosage titration [see Dosage and Administration (2.2)], or interferon (IFN) beta-1a, the active comparator, 30 mcg given intramuscularly once weekly. Neurological evaluations were performed at baseline, every 3 months, and at the time of a suspected relapse. Brain MRI scans were performed at baseline, 6 months (Study 1), 1 year (Studies 1 and 2), and 2 years (Study 2).

The primary endpoint of both Study 1 and Study 2 was the annualized relapse rate (ARR) over the treatment period (Study 1) and 24 months (Study 2). Additional outcome measures included: 1) the number of new or enlarging MRI T2 hyperintense lesions over 12 and 24 months, 2) the number of MRI T1 Gadolinium-enhancing (Gd+) lesions at 12 and 24 months, and 3) the time to confirmed disability progression, defined as at least a 1-point increase from baseline EDSS confirmed after 3 months and after 6 months. Confirmed disability progression was evaluated in a pooled analysis of Studies 1 and 2.

In Study 1, a total of 895 patients were randomized to receive ZEPOSIA (n=447) or IFN beta-1a (n=448); of these patients, 94% who received ZEPOSIA and 92% who received IFN beta-1a completed the study. The mean age was 35.4 years, 99.8% were White, and 65% were female. The mean time since MS symptom-onset was 6.9 years, and the median EDSS score at baseline was 2.5; 31% had been treated with a non-steroid therapy for MS. At baseline, the mean number of relapses in the prior year was 1.3 and 48% of patients had one or more T1 Gd-enhancing lesions (mean 1.8) on their baseline MRI scan.

In Study 2, a total of 874 patients were randomized to receive ZEPOSIA (n=433) or IFN beta-1a (n=441); of these patients, 90% who received ZEPOSIA and 85% who received IFN beta-1a completed the study. The mean age was 35.6 years, 98% were White, and 68% were female. The mean time since MS symptom onset was 6.6 years, and the median EDSS score at baseline was 2.5; 29% of patients had been treated with a non-steroid therapy for MS. At baseline, the mean number of relapses in the prior year was 1.3 and 43% of patients had one or more T1 Gd-enhancing lesions (mean 1.7).

The ARR was statistically significantly lower in patients treated with ZEPOSIA 0.92 mg than in patients who received IFN beta-1a 30 mcg IM. The number of new or enlarging T2 lesions and the number of GdE lesions were statistically significantly lower in patients treated with ZEPOSIA 0.92 mg than in patients who received IFN beta-1a.

There was no statistically significant difference in the three-month and six-month confirmed disability progression between ZEPOSIA and IFN beta-1a-treated patients over 2 years.

The results for Study 1 and Study 2 are shown in Table 8.

Table 8: Clinical and MRI Endpoints from MS Study 1 and Study 2
Endpoints | Study 1 |  | Study 2
Endpoints | ZEPOSIA 0.92 mg (n=447) % | IFN beta-1a 30 mcg (n=448) % | ZEPOSIA 0.92 mg (n=433) % | IFN beta-1a 30 mcg (n=441) %
Clinical Endpoints
Annualized Relapse Rate (Primary Endpoint) | 0.181a | 0.350 a | 0.172 | 0.276
Relative Reduction | 48% (p<0.0001) |  | 38% (p<0.0001)
Percentage of patients without relapseb | 78% | 66% | 76% | 64%
Proportion of Patients with 3-Month Confirmed Disability Progressionc,d | 7.6% ZEPOSIA vs. 7.8% IFN beta-1a
Hazard Ratio | 0.95 (p=0.77)e
MRI Endpoints
Mean number of new or enlarging T2 hyperintense lesions per MRIf | 1.47 | 2.84 | 1.84 | 3.18
Relative Reduction | 48% (p<0.0001) |  | 42% (p<0.0001)
Mean number of T1 Gd-enhancing lesionsg | 0.16 | 0.43 | 0.18 | 0.37
Relative Reduction | 63% (p<0.0001) |  | 53% (p=0.0006)
a Through the treatment period (mean duration 13.6 months).
b Over treatment period for Study 1 and over 24 months for Study 2.
c Disability progression defined as 1-point increase in Expanded Disability Status Scale (EDSS) confirmed 3 months or 6 months later.
d Prospective planned pooled analysis of Studies 1 and 2.
e Not statistically significant.
f Over 12 months for Study 1 and over 24 months for Study 2.
g At 12 months for Study 1 and at 24 months for Study 2.

A similar effect of ZEPOSIA on the ARR compared to IFN beta-1a was observed in exploratory subgroups defined by sex, age, prior non-steroid therapy for MS, and baseline disease activity.

14.2 Ulcerative Colitis

The efficacy and safety of ZEPOSIA were evaluated in two multicenter, randomized, double-blind, placebo-controlled clinical studies [UC Study 1 (induction) and UC Study 2 (maintenance) (NCT02435992)] in adult patients with moderately to severely active ulcerative colitis.

UC Study 1

In UC Study 1, a total of 645 patients were randomized 2:1 to either ZEPOSIA 0.92 mg given orally once daily or placebo for 10 weeks, beginning with a dosage titration [see Dosage and Administration (2.2)]. The trial included adult patients with moderately to severely active UC who had an inadequate response or were intolerant to any of the following: oral aminosalicylates, corticosteroids, immunomodulators (e.g., 6-mercaptopurine and azathioprine), or a biologic (e.g., TNF blocker and/or vedolizumab). Patients were required to be on stable doses of oral aminosalicylates and/or corticosteroids (prednisone daily dose up to 20 mg equivalent or budesonide extended-release tablets) prior to enrollment. Seventy-one percent of patients were receiving mesalamine, 13% sulfasalazine, and 33% oral corticosteroids. A total of 30% of patients had previously failed or were intolerant to TNF blockers. Of these patients, 63% received at least two biologics including TNF blockers.

The disease activity was assessed by the Mayo score (0 to 12) which consists of four subscores (0 to 3 for each subscore): stool frequency, rectal bleeding, findings on centrally-read endoscopy, and physician global assessment. An endoscopy subscore of 2 was defined by marked erythema, lack of vascular pattern, friability, and erosions; an endoscopy subscore of 3 was defined by spontaneous bleeding and ulceration. Enrolled patients had Mayo scores between 6 to 12; at baseline, patients had a median Mayo score of 9, with 86% of patients having moderate disease (Mayo score 6-10), and 14% having severe disease (Mayo score 11-12).

Concomitant immunomodulators or biologic therapies were not permitted.

The primary endpoint was clinical remission at Week 10, defined using a 3-component Mayo score without the physician global assessment: rectal bleeding subscore = 0, stool frequency subscore = 0 or 1 (and a decrease of ≥ 1 point from the baseline stool frequency subscore), and endoscopy subscore = 0 or 1 (an endoscopy subscore of 0 defined as normal or inactive disease, and an endoscopy subscore of 1 defined as presence of erythema, decreased vascular pattern and no friability).

The secondary endpoints were clinical response, endoscopic improvement, and endoscopic-histologic mucosal improvement. Clinical response (reduction from baseline in the 3-component Mayo score of ≥ 2 points and ≥ 35%, and a reduction from baseline in the rectal bleeding subscore of ≥ 1 point or an absolute rectal bleeding subscore of 0 or 1), endoscopic improvement (Mayo endoscopy subscore of 0 or 1), and endoscopic-histologic mucosal improvement [combined endoscopic improvement and histologic improvement of colonic tissue (no neutrophils in the epithelial crypts or lamina propria and no increase in eosinophils, no crypt destruction, and no erosions, ulcerations, or granulation tissue, i.e., Geboes < 2.0)].

A significantly greater proportion of patients treated with ZEPOSIA achieved clinical remission, clinical response, endoscopic improvement, and endoscopic-histologic mucosal improvement compared to placebo at Week 10 (see Table 9).

Table 9: Proportion of Patients Meeting Efficacy Endpoints in the Induction Period at Week 10 in UC Study 1
Endpoint | ZEPOSIA 0.92 mg Once Dailya (N=429) |  | Placebo (N=216) |  | Treatment Differenceb (95% CI)
Endpoint | n | % | n | % | Treatment Differenceb (95% CI)
Clinical remissionc | 79 | 18% | 13 | 6% | 12% (8%, 17%)g
Without prior TNF blocker exposure | 66/299 | 22% | 10/151 | 7%
Prior TNF blocker exposure | 13/130 | 10% | 3/65 | 5%
Clinical responsed | 205 | 48% | 56 | 26% | 22% (14%, 29%)g
Without prior TNF blocker exposure | 157/299 | 53% | 44/151 | 29%
Prior TNF blocker exposure | 48/130 | 37% | 12/65 | 19%
Endoscopic improvemente | 117 | 27% | 25 | 12% | 16% (10%, 22%)g
Without prior TNF blocker exposure | 97/299 | 32% | 18/151 | 12%
Prior TNF blocker exposure | 20/130 | 15% | 7/65 | 11%
Endoscopic-histologic mucosal improvementf | 54 | 13% | 8 | 4% | 9% (5%, 13%)h
Without prior TNF blocker exposure | 47/299 | 16% | 6/151 | 4%
Prior TNF blocker exposure | 7/130 | 5% | 2/65 | 3%
CI = confidence interval; TNF = tumor necrosis factor.
a ZEPOSIA was initiated with a 7-day titration [see Dosage and Administration (2.2)].
b Treatment difference (adjusted for stratification factors of prior anti-TNF exposure and corticosteroid use at baseline).
c Clinical remission is defined as: rectal bleeding subscore = 0, stool frequency subscore = 0 or 1 (and a decrease from baseline in the stool frequency subscore of ≥ 1 point), and endoscopy subscore = 0 or 1 without friability.
d Clinical response is defined as a reduction from baseline in the 3-component Mayo score of ≥ 2 points and ≥ 35%, and a reduction from baseline in the rectal bleeding subscore of ≥ 1 point or an absolute rectal bleeding subscore of 0 or 1.
e Endoscopic improvement is defined as a Mayo endoscopy subscore of 0 or 1 without friability.
f Endoscopic-histologic mucosal improvement is defined as both Mayo endoscopic subscore of 0 or 1 without friability and histologic improvement of colonic tissue (defined as no neutrophils in the epithelial crypts or lamina propria and no increase in eosinophils, no crypt destruction, and no erosions, ulcerations, or granulation tissue, i.e., Geboes < 2.0).
g p<0.0001.
h p<0.001.

The relationship of endoscopic-histologic mucosal improvement, as defined in UC Study 1, at Week 10 to disease progression and long term outcomes was not evaluated during UC Study 1.

Rectal Bleeding Subscore and Stool Frequency Subscores

Decreases in rectal bleeding and stool frequency subscores were observed as early as Week 2 (i.e., 1 week after completing the required 7-day dosage titration) in patients treated with ZEPOSIA.

UC Study 2

In UC Study 2, a total of 457 patients who received ZEPOSIA in either UC Study 1 or in an open-label arm and achieved clinical response at Week 10 were re-randomized 1:1 and were treated with either ZEPOSIA 0.92 mg (n=230) or placebo (n=227) for 42 weeks (UC Study 2), for a total of 52 weeks of treatment.

Patients were permitted to be on stable doses of oral aminosalicylates. Corticosteroid tapering was required upon entering this study for patients who were receiving corticosteroids during the induction period. Concomitant oral immunomodulators or biologic therapies were not permitted. At study entry, 35% of patients were in clinical remission; 29% of patients were on corticosteroids; and 31% of patients had an inadequate response, loss of response, or intolerance to TNF blockers.

The primary endpoint was the proportion of patients in clinical remission at Week 52. The secondary endpoints at Week 52 were the proportion of patients with clinical response, endoscopic improvement, endoscopic-histologic mucosal improvement, corticosteroid-free clinical remission, and maintenance of clinical remission at Week 52 among patients who achieved clinical remission at Week 10 in UC Study 1.

The results of the efficacy endpoints in the maintenance period are shown in Table 10.

Table 10: Proportion of Patients Meeting Efficacy Endpoints in the Maintenance Period at Week 52 in UC Study 2
Endpoint | ZEPOSIA 0.92 mg Once Dailya (N=230) |  | Placebo (N=227) |  | Treatment Differenceb (95% CI)
Endpoint | n | % | n | % | Treatment Differenceb (95% CI)
Clinical remissionc | 85 | 37% | 42 | 19% | 19% (11%, 26%)i
Without prior TNF blocker exposure | 63/154 | 41% | 35/158 | 22%
Prior TNF blocker exposure | 22/76 | 29% | 7/69 | 10%
Clinical responsed | 138 | 60% | 93 | 41% | 19% (10%, 28%)i
Without prior TNF blocker exposure | 96/154 | 62% | 76/158 | 48%
Prior TNF blocker exposure | 42/76 | 55% | 17/69 | 25%
Endoscopic improvemente | 105 | 46% | 60 | 26% | 19% (11%, 28%)j
Without prior TNF blocker exposure | 77/154 | 50% | 48/158 | 30%
Prior TNF blocker exposure | 28/76 | 37% | 12/69 | 17%
Maintenance of clinical remission at Week 52 in the subset of patients in remission at Week 10f | 41/79 | 52% | 22/75 | 29% | 24% (9%, 39%)k
Without prior TNF blocker exposure | 37/64 | 58% | 19/58 | 33%
Prior TNF blocker exposure | 4/15 | 27% | 3/17 | 18%
Corticosteroid-free clinical remissiong | 73 | 32% | 38 | 17% | 15% (8%, 23%)j
Without prior TNF blocker exposure | 55/154 | 36% | 31/158 | 20%
Prior TNF blocker exposure | 18/76 | 24% | 7/69 | 10%
Endoscopic-histologic mucosal improvementh | 68 | 30% | 32 | 14% | 16% (8%, 23%)j
Without prior TNF blocker exposure | 51/154 | 33% | 28/158 | 18%
Prior TNF blocker exposure | 17/76 | 22% | 4/69 | 6%
CI = confidence interval; TNF = tumor necrosis factor.
a ZEPOSIA was initiated with a 7-day titration [see Dosage and Administration (2.2)].
b Treatment difference (adjusted for stratification factors of clinical remission and concomitant corticosteroid use at Week 10).
c Clinical remission is defined as: rectal bleeding subscore = 0, stool frequency subscore = 0 or 1 (and a decrease from baseline in the stool frequency subscore of ≥ 1 point), and endoscopy subscore = 0 or 1 without friability.
d Clinical response is defined as a reduction from baseline in the 3-component Mayo score of ≥ 2 points and ≥ 35%, and a reduction from baseline in the rectal bleeding subscore of ≥ 1 point or an absolute rectal bleeding subscore of 0 or 1.
e Endoscopic improvement is defined as a Mayo endoscopy subscore of 0 or 1 without friability.
f Maintenance of remission is defined as clinical remission at Week 52 in the subset of patients in clinical remission at Week 10.
g Corticosteroid-free remission is defined as clinical remission at Week 52 while off corticosteroids for ≥ 12 weeks.
h Endoscopic-histologic mucosal improvement is defined as both Mayo endoscopic score of 0 or 1 without friability and histologic improvement of colonic tissue (defined as no neutrophils in the epithelial crypts or lamina propria and no increase in eosinophils, no crypt destruction, and no erosions, ulcerations, or granulation tissue, i.e., Geboes <2.0).
i p<0.0001.
j p<0.001.
k p=0.0025.

The relationship of endoscopic-histologic mucosal improvement, as defined in UC Study 2, at Week 52 to disease progression and long term outcomes was not evaluated during UC Study 2.

16 HOW SUPPLIED/STORAGE AND HANDLING

16.1 How Supplied

ZEPOSIA is available as capsules in the following dosage strengths:

- 0.23 mg ozanimod: light grey opaque body/light grey opaque cap imprinted with black ink "OZA" on the cap and "0.23 mg" on the body
- 0.46 mg ozanimod: light grey opaque body/orange opaque cap imprinted with black ink "OZA" on the cap and "0.46 mg" on the body
- 0.92 mg ozanimod: orange opaque body/orange opaque cap imprinted with black ink "OZA" on the cap and "0.92 mg" on the body

Capsules are supplied in the following strengths and package configurations:

Package configuration | Tablet strength | NDC number
Bottles of 30 | 0.92 mg ozanimod | 59572-820-30
7-Day Starter Pack | 7-capsule starter pack containing: (4) 0.23 mg ozanimod capsules and (3) 0.46 ozanimod mg capsules | 59572-810-07
Starter Kit (7-Day Starter Pack and 0.92 mg 30-count Bottle) | 37-capsule starter kit including: one 7-capsule starter pack containing: (4) 0.23 mg ozanimod capsules and (3) 0.46 mg ozanimod capsules and one bottle containing: (30) 0.92 mg ozanimod capsules | 59572-890-91 59572-890-07 59572-890-30
Starter Kit; (7-Day Starter Pack and 0.92 mg 21-count Bottle) | 28-capsule starter kit including: one 7-capsule starter pack containing: (4) 0.23 mg ozanimod capsules and (3) 0.46 mg ozanimod capsules and one bottle containing: (21) 0.92 mg ozanimod capsules | 59572-890-28 59572-890-07 59572-890-21

16.2 Storage

Store at 20°C to 25°C (68°F to 77°F); excursions permitted between 15°C to 30°C (59°F to 86°F) [see USP Controlled Room Temperature].

17 PATIENT COUNSELING INFORMATION

Advise the patient to read the FDA-approved patient labeling (Medication Guide).

Risk of Infections

Inform patients that they may be more likely to get infections, some of which could be life-threatening, when taking ZEPOSIA and for 3 months after stopping it, and that they should contact their healthcare provider if they develop symptoms of infection [see Warnings and Precautions (5.1)]. Inform patients that prior or concomitant use of drugs that suppress the immune system may increase the risk of infection. Advise patients that some vaccines containing live virus (live attenuated vaccines) should be avoided during treatment with ZEPOSIA. Advise patients that if immunizations are planned, they should be administered at least 1 month prior to initiation of ZEPOSIA. Inform patients that the use of live attenuated vaccines should be avoided during and for 3 months after treatment with ZEPOSIA.

Progressive Multifocal Leukoencephalopathy

Inform patients that cases of progressive multifocal leukoencephalopathy (PML) have occurred in patients who received ZEPOSIA and other S1P receptor modulators. Inform the patient that PML is characterized by a progression of deficits and usually leads to death or severe disability over weeks or months. Instruct the patient of the importance of contacting their healthcare provider if they develop any symptoms suggestive of PML. Inform the patient that typical symptoms associated with PML are diverse, progress over days to weeks, and include progressive weakness on one side of the body or clumsiness of limbs, disturbance of vision, and changes in thinking, memory, and orientation leading to confusion and personality changes [see Warnings and Precautions (5.2)].

Cardiac Effects

Advise patients that initiation of ZEPOSIA treatment may result in a transient decrease in heart rate. Inform patients that to reduce this effect, dose titration is required. Advise patients that the dose titration is also required if a dose is missed for 1 day or more during the first 14 days of treatment [see Dosage and Administration (2.2, 2.4) and Warnings and Precautions (5.3)].

Liver Injury

Inform patients that ZEPOSIA may cause liver injury. Advise patients that they should contact their healthcare provider if they have any unexplained nausea, vomiting, abdominal pain, fatigue, anorexia, or jaundice and/or dark urine [see Warnings and Precautions (5.4)].

Pregnancy and Fetal Risk

Inform patients that, based on animal studies, ZEPOSIA may cause fetal harm. Discuss with women of childbearing age whether they are pregnant, might be pregnant, or are trying to become pregnant. Advise women of childbearing potential of the need for effective contraception during treatment with ZEPOSIA and for 3 months after stopping ZEPOSIA. Advise a female patient to immediately inform her healthcare provider if she is pregnant or planning to become pregnant [see Warnings and Precautions (5.5) and Use in Specific Populations (8.3)].

Pregnancy Registry

Encourage multiple sclerosis patients to enroll in the ZEPOSIA Pregnancy Registry if they become pregnant while taking ZEPOSIA [see Use in Specific Populations (8.1)].

Respiratory Effects

Advise patients that they should contact their healthcare provider if they experience new onset or worsening dyspnea [see Warnings and Precautions (5.7)].

Macular Edema

Advise patients that ZEPOSIA may cause macular edema, and that they should obtain an eye exam near the start of treatment with ZEPOSIA, have their eyes monitored periodically by an eye care professional while receiving therapy, and contact their healthcare provider if they experience any changes in their vision while taking ZEPOSIA. Inform patients with diabetes mellitus or a history of uveitis that their risk of macular edema may be increased [see Warnings and Precautions (5.8)].

Cutaneous Malignancies

Inform patients that the risk of basal cell carcinoma, squamous cell carcinoma, and melanoma is increased in patients treated with S1P receptor modulators. Advise patients that any suspicious skin lesions should be promptly evaluated. Advise patients to limit exposure to sunlight and ultraviolet light by wearing protective clothing and using a sunscreen with high protection factor [see Warnings and Precautions (5.9)].

Posterior Reversible Encephalopathy Syndrome

Advise patients to immediately report to their healthcare provide any symptoms involving sudden onset of severe headache, altered mental status, visual disturbances, or seizure. Inform patients that delayed treatment could lead to permanent neurological consequences [see Warnings and Precautions (5.10)].

Severe Increase in Multiple Sclerosis Disability after Stopping ZEPOSIA

Inform patients with multiple sclerosis that severe increase in disability has been reported after discontinuation of a S1P receptor modulator like ZEPOSIA. Advise patients to contact their physician if they develop worsening symptoms of MS following discontinuation of ZEPOSIA [see Warnings and Precautions (5.12)].

Immune System Effects after Stopping ZEPOSIA

Advise patients that ZEPOSIA continues to have effects, such as lowering effects on peripheral lymphocyte count, for up to 3 months after the last dose [see Warnings and Precautions (5.13)].

Marketed by:
Bristol-Myers Squibb Company
Princeton, NJ 08543 USA

ZEPOSIA® is a trademark of Celgene Corporation, a Bristol-Myers Squibb company.

ZEPPI.012/ZEPMG.009

MEDICATION GUIDE
ZEPOSIA® (zeh-poe'-see-ah)
(ozanimod)
capsules, for oral use

Read this Medication Guide before you start taking ZEPOSIA and each time you get a refill. There may be new information. This Medication Guide does not take the place of talking with your healthcare provider about your medical condition or treatment.

What is the most important information I should know about ZEPOSIA?
ZEPOSIA may cause serious side effects, including:

1. Infections. ZEPOSIA can increase your risk of serious infections that can be life-threatening and cause death. ZEPOSIA lowers the number of white blood cells (lymphocytes) in your blood. This will usually go back to normal within 3 months of stopping treatment. Your healthcare provider may do a blood test of your white blood cells before you start taking ZEPOSIA.
  Call your healthcare provider right away if you have any of the following symptoms of an infection during treatment with ZEPOSIA and for 3 months after your last dose of ZEPOSIA:

- fever
- feeling very tired
- flu-like symptoms
- cough
- painful and frequent urination (signs of a urinary tract infection)
- rash

- headache with fever, neck stiffness, sensitivity to light, nausea or confusion (these may be symptoms of meningitis, an infection of the lining around your brain and spine)

Your healthcare provider may delay starting or may stop your ZEPOSIA treatment if you have an infection.

2. Progressive multifocal leukoencephalopathy (PML). ZEPOSIA can increase your risk for PML, which is a rare brain infection that usually leads to death or severe disability. If PML happens, it usually happens in people with weakened immune systems but has happened in people who do not have weakened immune systems. Symptoms of PML get worse over days to weeks. Call your doctor right away if you have any new or worsening symptoms of PML that have lasted several days, including:

- weakness on 1 side of your body
- loss of coordination in your arms or legs
- decreased strength
- problems with balance

- changes in your vision
- changes in your thinking or memory
- confusion
- changes in your personality

3. Slow heart rate (also known as bradyarrhythmia) when you start taking ZEPOSIA. ZEPOSIA may cause your heart rate to temporarily slow down, especially during the first 8 days that you take ZEPOSIA. You will have a test to check the electrical activity of your heart called an electrocardiogram (ECG) before you take your first dose of ZEPOSIA. Call your healthcare provider if you experience the following symptoms of slow heart rate:

- dizziness
- lightheadedness
- feeling like your heart is beating slowly or skipping beats

- shortness of breath
- confusion
- chest pain
- tiredness

Follow directions from your healthcare provider when starting ZEPOSIA and when you miss a dose. See "How should I take ZEPOSIA?".

See "What are possible side effects of ZEPOSIA?" for more information about side effects.

What is ZEPOSIA?
ZEPOSIA is a prescription medicine used to treat:

- adults with relapsing forms of multiple sclerosis (MS), to include clinically isolated syndrome, relapsing-remitting disease, and active secondary progressive disease.
- adults with moderately to severely active ulcerative colitis.

It is not known if ZEPOSIA is safe and effective in children.

Do not take ZEPOSIA if you:

- have had a heart attack, chest pain (unstable angina), stroke or mini-stroke (transient ischemic attack or TIA), or certain types of heart failure in the last 6 months.
- have or have had a history of certain types of an irregular or abnormal heartbeat (arrhythmia) that is not corrected by a pacemaker.
- have untreated, severe breathing problems during your sleep (sleep apnea).
- take certain medicines called monoamine oxidase (MAO) inhibitors (such as selegiline, phenelzine, linezolid).

Talk to your healthcare provider before taking ZEPOSIA if you have any of these conditions or do not know if you have any of these conditions.

Before taking ZEPOSIA, tell your healthcare provider about all of your medical conditions, including if you:

- have a fever or infection, or you are unable to fight infections due to a disease, or take or have taken medicines that lower your immune system.
- received a vaccine in the past 30 days or are scheduled to receive a vaccine. ZEPOSIA may cause vaccines to be less effective.
- Before you start treatment with ZEPOSIA, your healthcare provider may give you a chicken pox (Varicella Zoster Virus) vaccine if you have not had one before.
- have had chickenpox or have received the vaccine for chickenpox. Your healthcare provider may do a blood test for the chickenpox virus. You may need to get the full course of the vaccine for chickenpox and then wait 1 month before you start taking ZEPOSIA.
- have a slow heart rate.
- have an irregular or abnormal heartbeat (arrhythmia).
- have a history of a stroke.
- have heart problems, including a heart attack or chest pain.
- have high blood pressure.
- have liver problems.
- have breathing problems, including during your sleep.
- have eye problems, especially an inflammation of the eye called uveitis.
- had or now have any types of skin cancer, including basal cell carcinoma (BCC), melanoma, or squamous cell carcinoma (SCC).
- have diabetes.
- are pregnant or plan to become pregnant. ZEPOSIA may harm your unborn baby. Talk with your healthcare provider if you are pregnant or plan to become pregnant. If you are a female who can become pregnant, you should use effective birth control during your treatment with ZEPOSIA and for 3 months after you stop taking ZEPOSIA. Talk with your healthcare provider about what birth control method is right for you during this time. Tell your healthcare provider right away if you become pregnant while taking ZEPOSIA or if you become pregnant within 3 months after you stop taking ZEPOSIA.
  Pregnancy Registry for MS patients: There is a pregnancy registry for women with multiple sclerosis who become pregnant during treatment with ZEPOSIA. If you become pregnant while taking ZEPOSIA, tell your healthcare provider right away. Talk to your healthcare provider about registering with the ZEPOSIA Pregnancy Registry. The purpose of this registry is to collect information about your health and your baby's health. Either you or your healthcare provider can enroll you in this registry by calling 1-877-301-9314 or visiting www.zeposiapregnancyregistry.com.
  Information regarding registration of pregnant women with UC will be made available in the future.
- are breastfeeding or plan to breastfeed. It is not known if ZEPOSIA passes into your breast milk. Talk to your healthcare provider about the best way to feed your baby if you take ZEPOSIA.

Tell your healthcare provider about all the medicines you take or have recently taken, including prescription and over-the-counter medicines, vitamins, and herbal supplements. Using ZEPOSIA with other medicines can cause serious side effects. Especially tell your healthcare provider if you take or have taken:

- medicines that affect your immune system, such as alemtuzumab
- medicines to control your heart rhythm (antiarrhythmics), or heart beat
- CYP2C8 inducers such as rifampin
- CYP2C8 inhibitors such as gemfibrozil (medicine to treat high fat in your blood)
- opioids (pain medicine)
- medicines to treat depression
- medicines to treat Parkinson's disease
- medicines to control your heart rate and blood pressure (beta blocker medicines and calcium channel blocker medicines)
- medicines called monoamine oxidase (MAO) inhibitors (such as selegiline, phenelzine, linezolid).

You should not receive live vaccines during treatment with ZEPOSIA, for at least 1 month before taking ZEPOSIA and for 3 months after you stop taking ZEPOSIA. Vaccines may not work as well when given during treatment with ZEPOSIA.
Talk with your healthcare provider if you are not sure if you take any of these medicines.
Know the medicines you take. Keep a list of them to show your healthcare provider and pharmacist when you get a new medicine.

How should I take ZEPOSIA?
You will receive a 7-day starter pack. You must start ZEPOSIA by slowly increasing doses over the first week. Follow the dose schedule in the table below. This may reduce the risk of slowing of the heart rate.

Days 1-4

Take 0.23 mg (capsule in light grey color) 1 time a day

Days 5-7

Take 0.46 mg (capsule in half-light grey and half-orange color) 1 time a day

Days 8 and thereafter

Take 0.92 mg (capsule in orange color) 1 time a day, or as directed by your healthcare provider

- Take ZEPOSIA exactly as your healthcare provider tells you to take it.
- Swallow ZEPOSIA capsules whole.
- Take ZEPOSIA with or without food.
- Do not stop taking ZEPOSIA without talking with your healthcare provider first.
- Do not skip a dose.
- Start taking ZEPOSIA with a 7-day starter pack.
- If you miss 1 or more days of your ZEPOSIA dose during the first 14 days of treatment, talk to your healthcare provider. You will need to begin with another ZEPOSIA 7-day starter pack.
- If you miss a dose of ZEPOSIA after the first 14 days of treatment, take the next scheduled dose the following day.

What are the possible side effects of ZEPOSIA?
ZEPOSIA may cause serious side effects, including:

- See "What is the most important information I should know about ZEPOSIA?"
- liver problems. ZEPOSIA may cause liver damage. Your healthcare provider will do blood tests to check your liver before you start taking ZEPOSIA and periodically during treatment. Call your healthcare provider right away if you have any of the following symptoms:

- unexplained nausea
- vomiting
- stomach area (abdominal) pain
- tiredness

- loss of appetite
- yellowing of the whites of your eyes or skin
- dark colored urine

- increased blood pressure. Your healthcare provider should check your blood pressure during treatment with ZEPOSIA. See "How should I take ZEPOSIA?" section for more information.
- breathing problems. Some people who take ZEPOSIA have shortness of breath. Call your healthcare provider right away if you have new or worsening breathing problems.
- a problem with your vision called macular edema. Macular edema can cause some of the same vision symptoms as a multiple sclerosis (MS) attack (optic neuritis). You may not notice any symptoms with macular edema. Your healthcare provider should test your vision around the time you start taking ZEPOSIA, periodically while you continue taking ZEPOSIA, and at any time you notice vision changes during treatment with ZEPOSIA. Your risk for macular edema is higher if you have diabetes or have had an inflammation of your eye called uveitis. Call your healthcare provider right away if you have any of the following symptoms:

- blurriness or shadows in the center of your vision
- sensitivity to light

- a blind spot in the center of your vision
- unusually colored vision

- types of skin cancer, including basal cell carcinoma, melanoma, and squamous cell carcinoma. Tell your healthcare provider if you have any changes in the appearance of your skin, including changes in a mole, a new darkened area on your skin, a sore that does not heal, or growths on your skin, such as a bump that may be shiny, pearly white, skin-colored, or pink. Your doctor should check your skin for any changes at the start of and during treatment with ZEPOSIA. Limit the amount of time you spend in sunlight and ultraviolet (UV) light. Wear protective clothing and use a sunscreen with a high sun protection factor.
- swelling and narrowing of blood vessels in your brain. A condition called PRES (Posterior Reversible Encephalopathy Syndrome) is a rare condition that has happened with ZEPOSIA and with drugs in the same class. Symptoms of PRES usually get better when you stop taking ZEPOSIA. If left untreated, it may lead to a stroke. Your healthcare provider will do a test if you have any symptoms of PRES. Call your healthcare provider right away if you have any of the following symptoms:

- sudden severe headache
- sudden confusion

- sudden loss of vision or other changes in your vision
- seizure

- severe worsening of multiple sclerosis (MS) after stopping ZEPOSIA. When ZEPOSIA is stopped, symptoms of MS may return and become worse compared to before or during treatment. Always talk to your healthcare provider before you stop taking ZEPOSIA for any reason. Tell your healthcare provider if you have worsening symptoms of MS after stopping ZEPOSIA.

The most common side effects of ZEPOSIA can include:

- upper respiratory tract infections
- elevated liver enzymes

- low blood pressure when you stand up (orthostatic hypotension)
- painful and frequent urination (signs of urinary tract infection)

- back pain
- high blood pressure

- headache

These are not all of the possible side effects of ZEPOSIA. For more information, ask your healthcare provider or pharmacist. Call your doctor for medical advice about side effects. You may report side effects to FDA at 1-800-FDA-1088.

How should I store ZEPOSIA?

- Store ZEPOSIA at room temperature between 68°F to 77°F (20°C to 25°C).

Keep ZEPOSIA and all medicines out of the reach of children.

General information about the safe and effective use of ZEPOSIA.
Medicines are sometimes prescribed for purposes other than those listed in a Medication Guide. Do not take ZEPOSIA for conditions for which it was not prescribed. Do not give ZEPOSIA to other people, even if they have the same symptoms you have. It may harm them. You can ask your healthcare provider or pharmacist for information about ZEPOSIA that is written for health professionals.

What are the ingredients in ZEPOSIA?
Active ingredient: ozanimod
Inactive ingredients: colloidal silicon dioxide, croscarmellose sodium, magnesium stearate, and microcrystalline cellulose.
The capsule shell contains: black iron oxide, gelatin, red iron oxide, titanium dioxide, and yellow iron oxide.
Marketed by: Bristol-Myers Squibb Company, Princeton, NJ 08543 USA.
ZEPOSIA® is a trademark of Celgene Corporation, a Bristol-Myers Squibb company.

This Medication Guide has been approved by the U.S. Food and Drug Administration.
Revised: 8/2024

ZEPMG.009

PRINCIPAL DISPLAY PANEL - 0.92 mg Capsule Bottle Label

NDC 59572-820-30

ZEPOSIA®
(ozanimod) capsules

0.92 mg

Dispense the accompanying
Medication Guide to each patient.

Rx only
30 Capsules

Bristol-Myers Squibb

PRINCIPAL DISPLAY PANEL - 7 Capsule Starter Pack Kit Carton

NDC 59572-810-07
Rx only

ZEPOSIA®
(ozanimod) capsules

7-DAY
STARTER PACK

This pack contains 7 capsules for dosing
over 7 days. The contents of this pack are
as follows:

Four 0.23 mg capsules
Three 0.46 mg capsules

7 CAPSULES

Dispense the accompanying Medication Guide to each patient.

Bristol-Myers Squibb

PRINCIPAL DISPLAY PANEL - Kit Carton

Rx only

NDC 59572-890-91

ZEPOSIA®
(ozanimod) capsules

STARTER KIT

STEP 1: (Days 1-7)

Starting at Day 1, complete the 7-Day Starter Pack
Days 1-4: Take one 0.23 mg capsule orally once daily
Days 5-7: Take one 0.46 mg capsule orally once daily

STEP 2: (Day 8 and thereafter)

After completing the 7-Day Starter Pack, begin taking
one 0.92 mg capsule once daily or as directed from the 30-count bottle.

This Starter Kit contains 37 capsules for titration
over 7 days up to prescribed maintenance dose
of one 0.92 mg capsule taken once daily or as directed. The
contents of the Starter Kit, which are not to be
sold separately, are as follows:

Four 0.23 mg capsules
Three 0.46 mg capsules
Thirty 0.92 mg capsules

37 CAPSULES

Dispense the accompanying Medication Guide to each patient.

Bristol Myers Squibb

Package/Label Display Panel

Rx only

NDC 59572-890-28

ZEPOSIA®
(ozanimod) capsules

STARTER KIT

STEP 1: (Days 1-7)

Starting at Day 1, complete the 7-Day Starter Pack
Days 1-4: Take one 0.23 mg capsule orally once daily
Days 5-7: Take one 0.46 mg capsule orally once daily

STEP 2: (Day 8 and thereafter)

After completing the 7-Day Starter Pack, begin
taking one 0.92 mg capsule a day or as directed
from the 21-count bottle.

This Starter Kit contains 28 capsules for titration
over 7 days up to prescribed maintenance dose
of one 0.92 mg capsule taken once daily or as
directed. The contents of the Starter Kit, which
are not to be sold separately, are as follows:

Four 0.23 mg capsules
Three 0.46 mg capsules
Twenty One 0.92 mg capsules

28 CAPSULES

Dispense the accompanying Medication Guide to each patient.

Bristol Myers Squibb